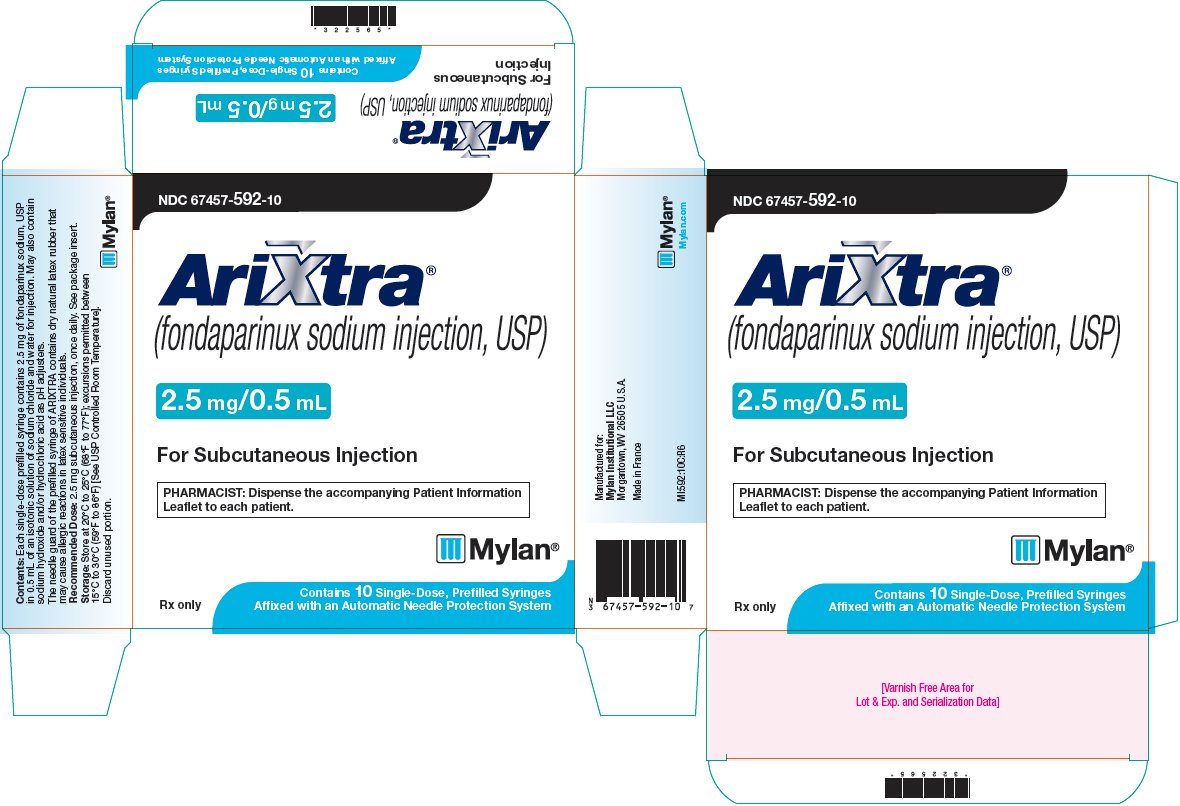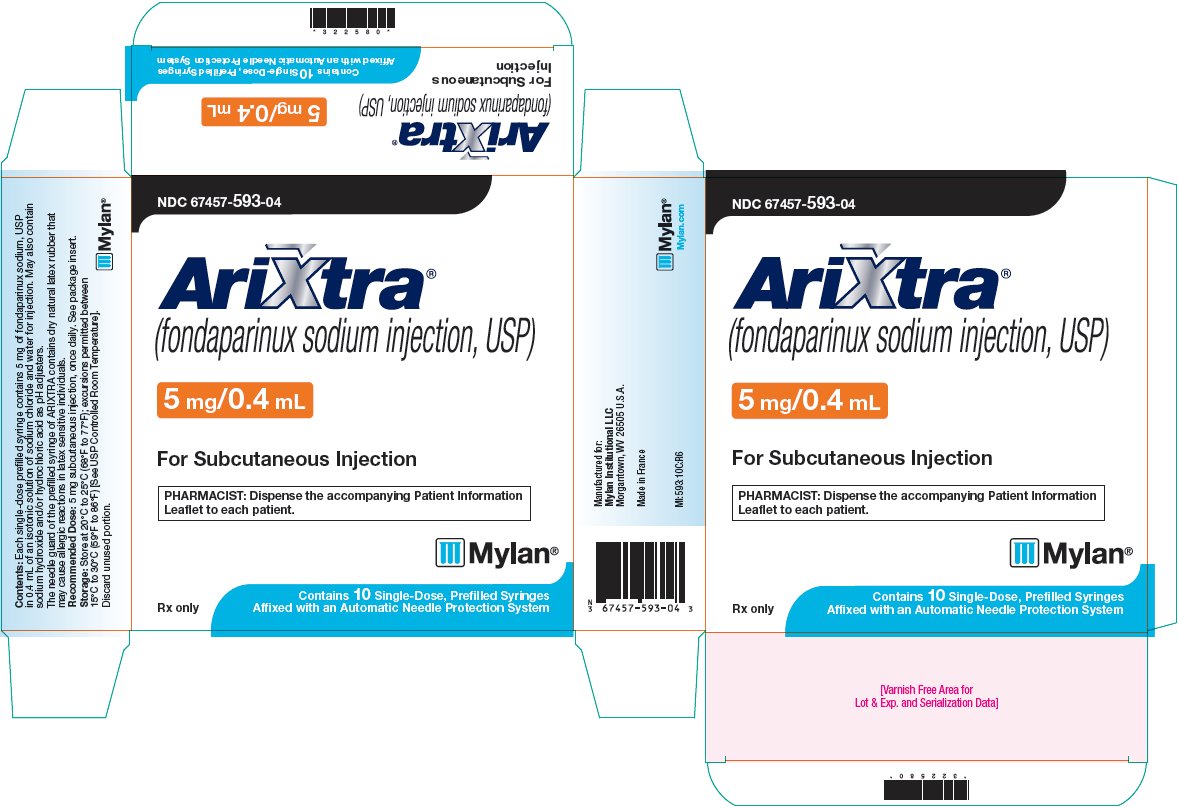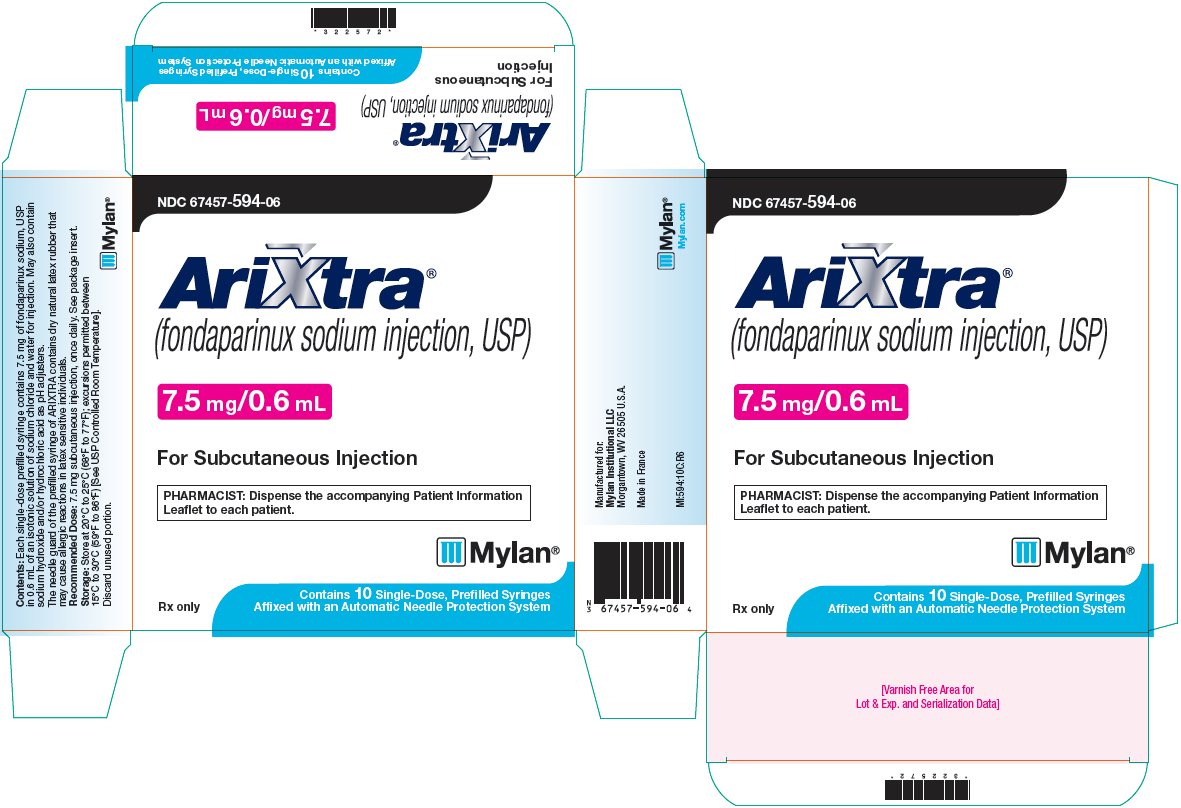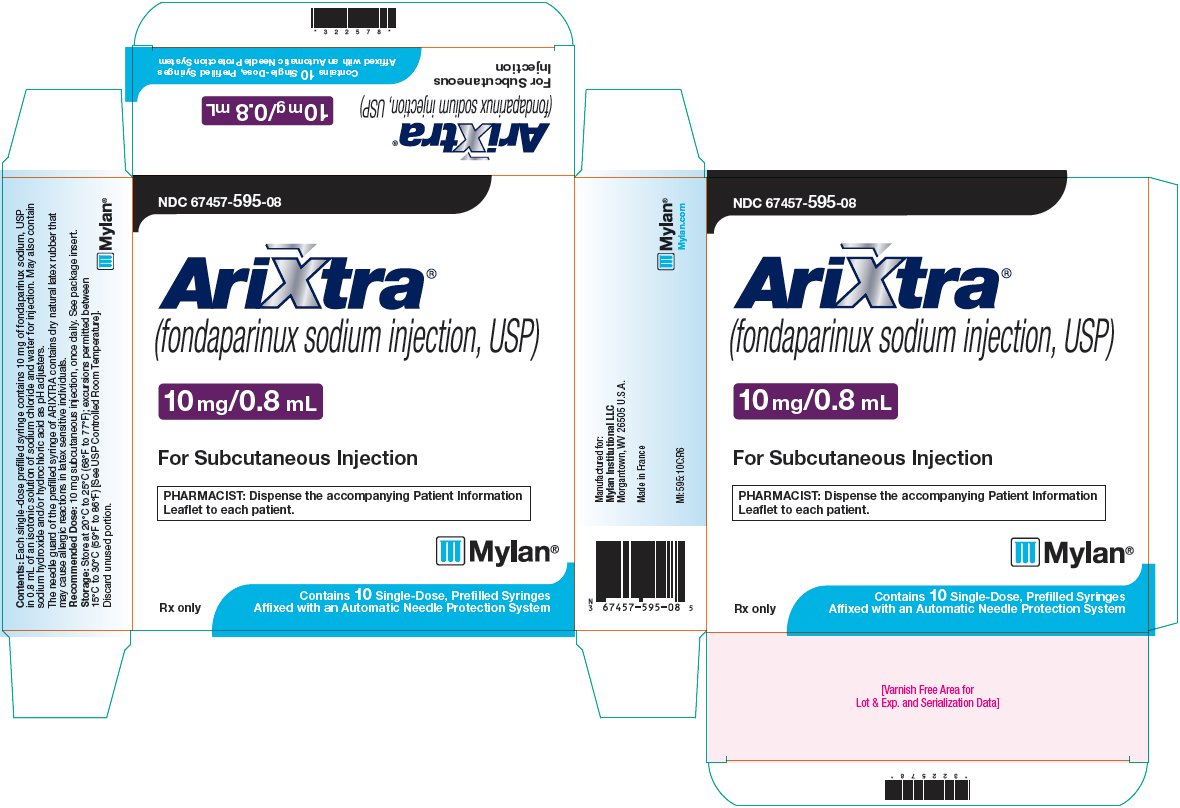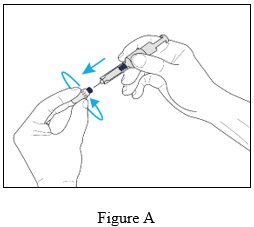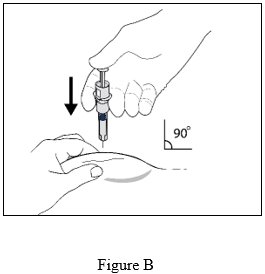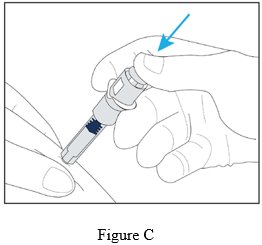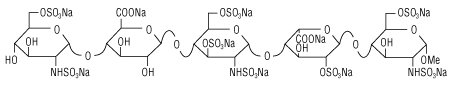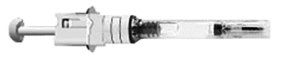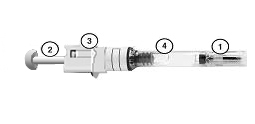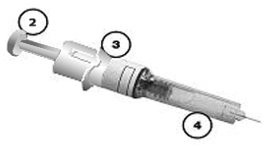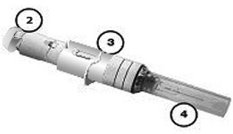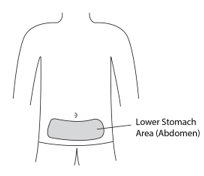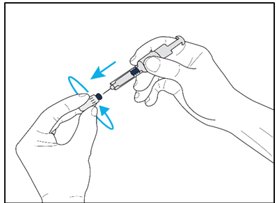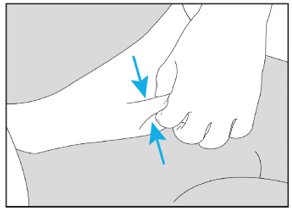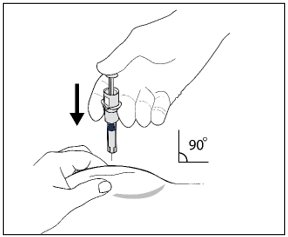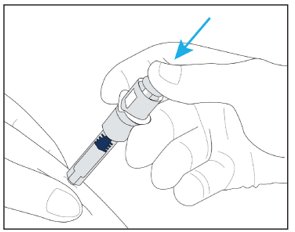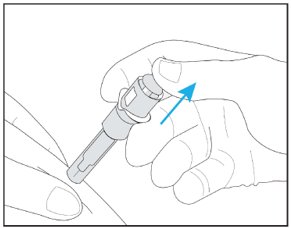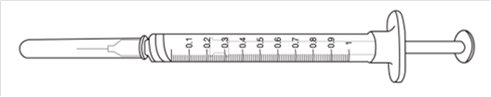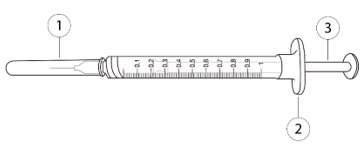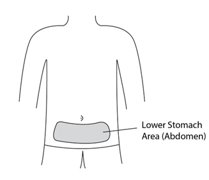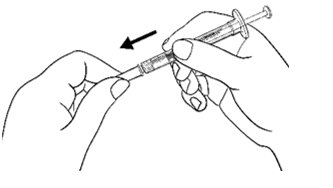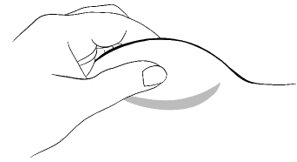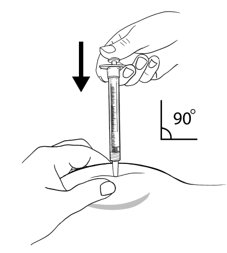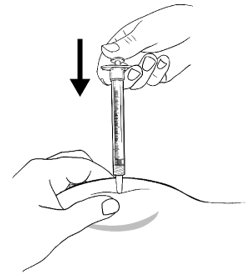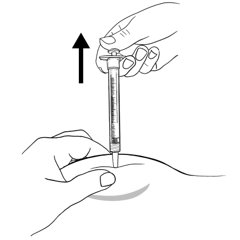 DRUG LABEL: Arixtra
NDC: 67457-592 | Form: INJECTION, SOLUTION
Manufacturer: Mylan Institutional LLC
Category: prescription | Type: HUMAN PRESCRIPTION DRUG LABEL
Date: 20241210

ACTIVE INGREDIENTS: FONDAPARINUX SODIUM 2.5 mg/0.5 mL
INACTIVE INGREDIENTS: SODIUM CHLORIDE; WATER

HIGHLIGHTS OF PRESCRIBING INFORMATION

These highlights do not include all the information needed to use ARIXTRA safely and effectively. See full prescribing information for ARIXTRA.
ARIXTRA (fondaparinux sodium injection), for subcutaneous use
Initial U.S. Approval: 2001

RECENT MAJOR CHANGES

Indications and Usage (1.4) 12/2024

Dosage and Administration (2.1, 2.5, 2.7, 2.8) 12/2024

Warnings and Precautions (5.2) 12/2024

WARNING: SPINAL/EPIDURAL HEMATOMAS

See full prescribing information for complete boxed warning.

Epidural or spinal hematomas may occur in patients who are anticoagulated with low molecular weight heparins (LMWH), heparinoids, or fondaparinux sodium and are receiving neuraxial anesthesia or undergoing spinal puncture. These hematomas may result in long-term or permanent paralysis. Consider these risks when scheduling patients for spinal procedures. Factors that can increase the risk of developing epidural or spinal hematomas in these patients include:

- use of indwelling epidural catheters
- concomitant use of other drugs that affect hemostasis, such as non-steroidal anti-inflammatory drugs (NSAIDs), platelet inhibitors, or other anticoagulants
- a history of traumatic or repeated epidural or spinal puncture
- a history of spinal deformity or spinal surgery

Monitor patients frequently for signs and symptoms of neurologic impairment. If neurologic compromise is noted, urgent treatment is necessary.

Consider the benefit and risks before neuraxial intervention in patients anticoagulated or to be anticoagulated for thromboprophylaxis [see Warnings and Precautions (5.1) and Drug Interactions (7)].

1 INDICATIONS AND USAGE

ARIXTRA is a Factor Xa inhibitor (anticoagulant) indicated for:

- Prophylaxis of deep vein thrombosis (DVT) in adult patients undergoing hip fracture surgery (including extended prophylaxis), hip replacement surgery, knee replacement surgery, or abdominal surgery. (1.1)
- Treatment of DVT or acute pulmonary embolism (PE) in adult patients when administered in conjunction with warfarin sodium. (1.2, 1.3)
- Treatment of venous thromboembolism (VTE) in pediatric patients aged 1 year or older weighing at least 10 kg. (1.4)

2 DOSAGE AND ADMINISTRATION

- For subcutaneous use, do not mix with other injections or infusions. (2.1)
- Prophylaxis of deep vein thrombosis in adults: ARIXTRA 2.5 mg subcutaneously once daily after hemostasis has been established. The initial dose should be given no earlier than 6 hours to 8 hours after surgery and continued for 5 days to 9 days. For patients undergoing hip fracture surgery, extended prophylaxis up to 24 additional days is recommended. (2.2, 2.3)
- Treatment of deep vein thrombosis and pulmonary embolism in adults: ARIXTRA 5 mg (body weight less than 50 kg), 7.5 mg (50 kg to 100 kg), or 10 mg (greater than 100 kg) subcutaneously once daily. Treatment should continue for at least 5 days until INR 2 to 3 is achieved with warfarin sodium. (2.4)
- Treatment of venous thromboembolism in pediatric patients weighing at least 10 kg: ARIXTRA 0.1 mg/kg subcutaneously once daily. (2.5)

3 DOSAGE FORMS AND STRENGTHS

Single-dose, prefilled syringes containing 2.5 mg/0.5 mL, 5 mg/0.4 mL, 7.5 mg/0.6 mL, or 10 mg/0.8 mL of fondaparinux sodium. (3)

4 CONTRAINDICATIONS

ARIXTRA is contraindicated in the following conditions: (4)

- Severe renal impairment (creatinine clearance less than 30 mL/min) in prophylaxis or treatment of venous thromboembolism.
- Active major bleeding.
- Bacterial endocarditis.
- Thrombocytopenia associated with a positive in vitro test for anti-platelet antibody in the presence of fondaparinux sodium.
- Body weight less than 50 kg (venous thromboembolism prophylaxis in adults only).
- History of serious hypersensitivity reaction (e.g., angioedema, anaphylactoid/anaphylactic reactions) to ARIXTRA.

5 WARNINGS AND PRECAUTIONS

- Spinal or epidural hematomas, which may result in long-term or permanent paralysis, can occur. (5.1)
- Patients taking ARIXTRA with risk factors for bleeding are at increased risk of hemorrhage. (5.2)
- Bleeding risk is increased in renal impairment and in adult patients with low body weight less than 50 kg. (5.3, 5.4)
- Thrombocytopenia can occur with administration of ARIXTRA. (5.5)
- Periodic routine complete blood counts (including platelet counts), serum creatinine level, and stool occult blood tests are recommended. (5.6)
- The packaging (needle guard) contains dry natural rubber and may cause allergic reactions in latex sensitive individuals. (5.7)

6 ADVERSE REACTIONS

The most serious adverse reactions associated with the use of ARIXTRA are bleeding complications. (6.1)

To report SUSPECTED ADVERSE REACTIONS, contact Mylan at 1-877-446-3679 (1-877-4-INFO-RX) or FDA at 1-800-FDA-1088 or www.fda.gov/medwatch.

7 DRUG INTERACTIONS

Discontinue agents that may enhance the risk of hemorrhage prior to initiation of therapy with ARIXTRA unless essential. If co-administration is necessary, monitor patients closely for hemorrhage. (7)

8 USE IN SPECIFIC POPULATIONS

- Because elderly patients are more likely to have reduced renal function, ARIXTRA should be used with caution in these patients. (8.5)
- The risk of bleeding is increased with reduced renal or hepatic function. (8.6, 8.7)

FULL PRESCRIBING INFORMATION

WARNING: SPINAL/EPIDURAL HEMATOMAS

Epidural or spinal hematomas may occur in patients who are anticoagulated with low molecular weight heparins (LMWH), heparinoids, or fondaparinux sodium and are receiving neuraxial anesthesia or undergoing spinal puncture. These hematomas may result in long-term or permanent paralysis. Consider these risks when scheduling patients for spinal procedures. Factors that can increase the risk of developing epidural or spinal hematomas in these patients include:

- use of indwelling epidural catheters
- concomitant use of other drugs that affect hemostasis, such as non-steroidal anti- inflammatory drugs (NSAIDs), platelet inhibitors, or other anticoagulants
- a history of traumatic or repeated epidural or spinal puncture
- a history of spinal deformity or spinal surgery
- Optimal timing between the administration of ARIXTRA and neuraxial procedures is not known.

Monitor patients frequently for signs and symptoms of neurologic impairment. If neurologic compromise is noted, urgent treatment is necessary.

Consider the benefit and risks before neuraxial intervention in patients anticoagulated or to be anticoagulated for thromboprophylaxis [see Warnings and Precautions (5.1) and Drug Interactions (7)].

1 INDICATIONS AND USAGE

1.1 Prophylaxis of Deep Vein Thrombosis in Adult Patients

ARIXTRA® is indicated for the prophylaxis of deep vein thrombosis (DVT) in adults, which may lead to pulmonary embolism (PE):

- in patients undergoing hip fracture surgery, including extended prophylaxis;
- in patients undergoing hip replacement surgery;
- in patients undergoing knee replacement surgery;
- in patients undergoing abdominal surgery who are at risk for thromboembolic complications.

1.2 Treatment of Acute Deep Vein Thrombosis in Adult Patients

ARIXTRA is indicated for the treatment of acute deep vein thrombosis in adults when administered in conjunction with warfarin sodium.

1.3 Treatment of Acute Pulmonary Embolism in Adult Patients

ARIXTRA is indicated for the treatment of acute pulmonary embolism in adults when administered in conjunction with warfarin sodium when initial therapy is administered in the hospital.

1.4 Treatment of Venous Thromboembolism in Pediatric Patients

ARIXTRA is indicated for the treatment of venous thromboembolism (VTE) in pediatric patients aged 1 year or older weighing at least 10 kg.

2 DOSAGE AND ADMINISTRATION

2.1 Important Dosing Information

Do not mix other medications or solutions with ARIXTRA. Administer ARIXTRA only subcutaneously. Discard unused portion.

Monitor routine complete blood counts (including platelet count), serum creatinine level, and stool occult blood periodically [see Warnings and Precautions (5.6)].

2.2 Deep Vein Thrombosis Prophylaxis Following Hip Fracture, Hip Replacement, and Knee Replacement Surgery in Adults

In adult patients undergoing hip fracture, hip replacement, or knee replacement surgery, the recommended dose of ARIXTRA is 2.5 mg administered by subcutaneous injection once daily after hemostasis has been established. Administer the initial dose no earlier than 6 hours to 8 hours after surgery. Administration of ARIXTRA earlier than 6 hours after surgery increases the risk of major bleeding. The usual duration of therapy is 5 days to 9 days; up to 11 days of therapy was administered in clinical trials.

In patients undergoing hip fracture surgery, an extended prophylaxis course of up to 24 additional days is recommended. In patients undergoing hip fracture surgery, a total of 32 days (peri-operative and extended prophylaxis) was administered in clinical trials [see Warnings and Precautions (5.6), Adverse Reactions (6), and Clinical Studies (14)].

2.3 Deep Vein Thrombosis Prophylaxis Following Abdominal Surgery in Adults

In adult patients undergoing abdominal surgery, the recommended dose of ARIXTRA is 2.5 mg administered by subcutaneous injection once daily after hemostasis has been established. Administer the initial dose no earlier than 6 hours to 8 hours after surgery. Administration of ARIXTRA earlier than 6 hours after surgery increases the risk of major bleeding. The usual duration of administration is 5 days to 9 days, and up to 10 days of ARIXTRA was administered in clinical trials.

2.4 Deep Vein Thrombosis and Pulmonary Embolism Treatment in Adults

In adult patients with acute symptomatic DVT and in patients with acute symptomatic PE, the recommended dose of ARIXTRA is 5 mg (body weight less than 50 kg), 7.5 mg (body weight 50 kg to 100 kg), or 10 mg (body weight greater than 100 kg) by subcutaneous injection once daily (ARIXTRA treatment regimen). Initiate concomitant treatment with warfarin sodium as soon as possible, usually within 72 hours. Continue treatment with ARIXTRA for at least 5 days and until a therapeutic oral anticoagulant effect is established (INR 2 to 3). The usual duration of administration of ARIXTRA is 5 days to 9 days; up to 26 days of ARIXTRA injection was administered in clinical trials [see Warnings and Precautions (5.6), Adverse Reactions (6), and Clinical Studies (14)].

2.5 Venous Thromboembolism Treatment in Pediatric Patients Aged 1 Year or Older Weighing at Least 10 kg

For patients weighing 10 kg to 20 kg, the recommended initial dose is 0.1 mg/kg subcutaneously once daily. There is no available prefilled syringe for patients in this weight range, and a patient specific dose should be prepared (see section 2.8 Instructions for Preparation of Individual Pediatric Doses in Pharmacies). The dose should be exact and rounded to the nearest 0.1 mg (see Table 1).

Table 1. Recommended Initial Dose of ARIXTRA for Treatment of VTE in Pediatric Patients Weighing 10 kg to 20 kg
Body Weight (kg) | Initial Dose
10 kg to 20 kg | Dosing should be exact and rounded to the nearest 0.1 mg

For patients weighing over 20 kg, the recommended initial dose is 0.1 mg/kg subcutaneously once daily with doses rounded to the nearest prefilled syringe according to Table 2.

There is no available information for dosing pediatric patients who weigh less than 10 kg.

Table 2. Recommended Prefilled Syringe Selection for Initial Dose of ARIXTRA for Treatment of VTE in Pediatric Patients Weighing More Than 20 kg
Body Weight (kg) | Prefilled Syringe Selection
Greater than 20 kg to 40 kg [Whenever possible, patients weighing more than 20 kg should receive a full prefilled syringe for dosing. If therapeutic levels are not achievable using the prefilled syringe available strengths and dose adjustments are needed, a patient specific dose may be prepared (see section 2.8 Instructions for Preparation of Individual Pediatric Doses in Pharmacies).] | 2.5 mg/0.5 mL
Greater than 40 kg to 60 kg | 5 mg/0.4 mL
Greater than 60 kg | 7.5 mg/0.6 mL

Monitor fondaparinux levels 2 hours to 4 hours after the second or third dose and then weekly for a month followed by every 1 month to 3 months for the duration of treatment using a fondaparinux-based anti-Xa assay with a therapeutic goal range of 0.5 mg/L to 1 mg/L.

Dosing adjustments may be necessary to achieve peak blood concentration within the therapeutic target of 0.5 mg/L to 1 mg/L (see Table 3). Do not exceed the maximum dose of 7.5 mg/day.

Table 3. Recommended Dose Adjustments
Fondaparinux-Based Anti-Xa Level (mg/L) | Dose Adjustment
Less than 0.3 mg/L | Increase dose by 0.03 mg/kg [Adjust the dose to the nearest 0.1 mg.]
0.3 mg/L to 0.49 mg/L | Increase dose by 0.01 mg/kg
0.5 mg/L to 1 mg/L | No change
1.01 mg/L to 1.2 mg/L | Decrease dose by 0.01 mg/kg
Greater than 1.2 mg/L | Decrease dose by 0.03 mg/kg

There is no adequate data to support the use of ARIXTRA in pediatric patients below 1 year of age.

2.6 Hepatic Impairment

No dose adjustment is recommended in patients with mild to moderate hepatic impairment, based upon single-dose pharmacokinetic data. Pharmacokinetic data are not available for patients with severe hepatic impairment. Patients with hepatic impairment may be particularly vulnerable to bleeding during ARIXTRA therapy. Observe these patients closely for signs and symptoms of bleeding [see Clinical Pharmacology (12.4)].

2.7 Instructions for Use for Prefilled Syringe

ARIXTRA Injection is provided in a single-dose, prefilled syringe affixed with an automatic needle protection system. ARIXTRA is administered by subcutaneous injection. It must not be administered by intramuscular injection. ARIXTRA is intended for use under a physician’s guidance. Patients may self-inject only if their physician determines that it is appropriate, and the patients are trained in subcutaneous injection techniques.

Prior to administration, visually inspect ARIXTRA to ensure the solution is clear and free of particulate matter.

To avoid the loss of drug when using the prefilled syringe, do not expel the air bubble from the syringe before the injection. Administration should be made in the fatty tissue, alternating injection sites (e.g., between the left and right anterolateral or the left and right posterolateral abdominal wall).

To administer ARIXTRA:

1. Wipe the surface of the injection site with an alcohol swab.
2. Hold the syringe with either hand and use your other hand to twist the rigid needle guard (covers the needle) counter-clockwise. Pull the rigid needle guard straight off the needle (Figure A). Discard the needle guard.

3. Do not try to remove the air bubbles from the syringe before giving the injection.
4. Pinch a fold of skin at the injection site between your thumb and forefinger and hold it throughout the injection.
5. Hold the syringe with your thumb on the top pad of the plunger rod and your next 2 fingers on the finger grips on the syringe barrel. Pay attention to avoid sticking yourself with the exposed needle.
6. Insert the full length of the syringe needle perpendicularly into the skin fold held between the thumb and forefinger (Figure B).

7. Push the plunger rod firmly with your thumb as far as it will go. This will ensure you have injected all the contents of the syringe (Figure C).

8. When you have injected all the contents of the syringe, the plunger should be released. The plunger will then rise automatically while the needle withdraws from the skin and retracts into the security sleeve. Discard the syringe into the sharps container.
9. You will know that the syringe has worked when:
  1. The needle is pulled back into the security sleeve and the white safety indicator appears above the upper body.
  2. You may also hear or feel a soft click when the plunger rod is released fully.

2.8 Instructions for Preparation of Individual Pediatric Doses in Pharmacies

For pediatric patients weighing 10 kg to 20 kg, a patient-specific dose may be prepared by a pharmacist under aseptic conditions per the instructions below.

These instructions may also be used to prepare pediatric patient-specific doses for patients weighing over 20 kg when dose adjustments are needed and therapeutic levels are not achievable using the prefilled syringe available strengths.

Prior to preparing ARIXTRA, visually inspect ARIXTRA prefilled syringe to ensure the solution is clear and free of particulate matter.

General Aseptic Preparation Practices

Strictly observe aseptic technique when preparing patient specific pediatric doses of ARIXTRA. To prevent accidental contamination, prepare ARIXTRA according to aseptic standards, including but not limited to:

- Prepare ARIXTRA in an ISO Class 5 laminar airflow (LAF) hood
- Ensure that the dose preparation area, including the LAF hood, has appropriate environmental specifications, confirmed by periodic monitoring.
- Ensure that personnel are appropriately trained in aseptic manipulations of sterile products.
- Ensure that personnel wear appropriate clothing and gloves.
- Ensure that gloves and surfaces are disinfected.

All steps should be completed in accordance with aseptic techniques:

1. Determine the total dose and volume per the duration, and the appropriate number of ARIXTRA prefilled syringes. One ARIXTRA prefilled syringe is used in cases where the total required dose is less than 0.5 mL. Where the total dose required is greater than or equal to 0.5 mL, only two ARIXTRA prefilled syringes may be pooled together. The maximum number of ARIXTRA prefilled syringes that may be pooled together is two.
  Do not combine ARIXTRA prefilled syringes of different concentrations in one injection to give the prescribed dose.
2. Gather the required supplies including the appropriate ARIXTRA prefilled syringe(s), a sterile, closed/sealed, empty glass vial (recommended 5 mL), and required number of suitable sized graduated tuberculin sterile syringes with 27 gauge x ½” staked needles or sterile needles (if not pre-attached to syringe).
3. Verify the required supplies are correct and within expiry date. Ensure only the materials required for the preparation are present in the work area.
4. While wearing sterile gloves, clean the LAF hood and wipe it down with sterile 70% alcohol. Ensure the LAF hood is within specification and continually monitored.
5. Ensure equipment and consumables are cleaned with isopropyl alcohol (IPA).
6. Before transferring into the LAF hood, clean all supplies including ancillary items (such as vial holder jigs, syringe cap holder jigs, sharps containers) with IPA.
7. Perform all the dose preparation steps within the LAF hood.
8. Pre-sterilize gloves with IPA. While wearing sterile gloves, hold the ARIXTRA prefilled syringe with either gloved hand and use your other gloved hand to twist the rigid needle guard (covers the needle) counter-clockwise. Pull the rigid needle guard straight off the needle. Discard the needle guard.
9. Dispense the full contents of the ARIXTRA prefilled syringe into the vial by fully depressing the plunger.
10. When you have injected all the contents of the ARIXTRA prefilled syringe, the plunger should be released. The plunger will then rise automatically while the needle retracts into the security sleeve. Discard the ARIXTRA prefilled syringe into a sharps container.
11. Take an empty graduated tuberculin sterile syringe and attach a suitable sterile needle if not already supplied pre-attached.
12. Remove needle cap.
13. Withdraw required dose from vial into the tuberculin syringe.
14. Replace needle cap over the needle. Clean the external surfaces of the filled tuberculin syringe with IPA.
15. Repeat steps 11 to 14 as required for the appropriate number of tuberculin syringes necessary for the patient.
16. Label each ARIXTRA tuberculin syringe with patient specific information (e.g., dosing instructions, patient information), storage information (e.g., store refrigerated between 36°F to 46°F (2°C to 8°C), do not freeze, and the beyond use date). The beyond use date should be the earlier of the product expiration date of the ARIXTRA prefilled syringe or 30 days after preparation of the tuberculin syringe.
17. Prepared tuberculin syringes may be dispensed in an empty plastic bag. Include Patient Information and Instructions for Use for the tuberculin syringe within the plastic bag to be dispensed to patients. They may be stored at refrigerated temperatures between 36°F to 46°F (2°C to 8°C) for up to the beyond use date. Do not freeze.
  Do not store the pediatric preparations at room temperature as they are growth promoting at room temperature.
  Discard unused portion.

3 DOSAGE FORMS AND STRENGTHS

Injection: Single-dose, prefilled syringes containing clear to practically clear and colorless liquid containing either 2.5 mg/0.5 mL, 5 mg/0.4 mL, 7.5 mg/0.6 mL, or 10 mg/0.8 mL of fondaparinux sodium.

4 CONTRAINDICATIONS

ARIXTRA is contraindicated in the following conditions:

- Severe renal impairment (creatinine clearance [CrCl] less than 30 mL/min) [see Warnings and Precautions (5.3) and Use in Specific Populations (8.6)].
- Active major bleeding.
- Bacterial endocarditis.
- Thrombocytopenia associated with a positive in vitro test for anti-platelet antibody in the presence of fondaparinux sodium.
- Body weight less than 50 kg (venous thromboembolism [VTE] prophylaxis in adults only) [see Warnings and Precautions (5.4)].
- History of serious hypersensitivity reaction (e.g., angioedema, anaphylactoid/anaphylactic reactions) to ARIXTRA.

5 WARNINGS AND PRECAUTIONS

5.1 Neuraxial Anesthesia and Post-operative Indwelling Epidural Catheter Use

Spinal or epidural hematomas, which may result in long-term or permanent paralysis, can occur with the use of anticoagulants and neuraxial (spinal/epidural) anesthesia or spinal puncture. The risk of these events may be higher with post-operative use of indwelling epidural catheters or concomitant use of other drugs affecting hemostasis such as NSAIDs [see Boxed Warning]. In the postmarketing experience, epidural or spinal hematoma has been reported in association with the use of ARIXTRA by subcutaneous (SC) injection. Optimal timing between the administration of ARIXTRA and neuraxial procedures is not known. Monitor patients undergoing these procedures for signs and symptoms of neurologic impairment such as midline back pain, sensory and motor deficits (numbness, tingling, or weakness in lower limbs), and bowel or bladder dysfunction. Consider the potential risks and benefits before neuraxial intervention in patients anticoagulated or who may be anticoagulated for thromboprophylaxis.

5.2 Hemorrhage

ARIXTRA increases the risk of hemorrhage in patients at risk for bleeding, including conditions such as congenital or acquired bleeding disorders, active ulcerative and angiodysplastic gastrointestinal disease, hemorrhagic stroke, uncontrolled arterial hypertension, diabetic retinopathy, or shortly after brain, spinal, or ophthalmological surgery. Cases of elevated aPTT temporally associated with bleeding events have been reported following administration of ARIXTRA (with or without concomitant administration of other anticoagulants) [see Adverse Reactions (6.2)].

Conditions associated with increased bleeding in pediatric patients include systemic lupus erythematosus, Wilms tumor, antiphospholipid syndrome, antithrombin III deficiency, Factor V Leiden, malignancy, pancytopenia, indwelling chest tubes, thoracotomy, invasive infections, hypertensive encephalopathy, intestinal lymphangiectasia and von Willebrand disease.

Do not administer agents that enhance the risk of hemorrhage with ARIXTRA unless essential for the management of the underlying condition, such as vitamin K antagonists for the treatment of VTE. If co-administration is essential, closely monitor patients for signs and symptoms of bleeding.

Do not administer the initial dose of ARIXTRA earlier than 6 to 8 hours after surgery. Administration earlier than 6 hours after surgery increases risk of major bleeding [see Dosage and Administration (2) and Adverse Reactions (6.1)].

5.3 Renal Impairment and Bleeding Risk in Adult Patients

ARIXTRA increases the risk of bleeding in adult patients with impaired renal function due to reduced clearance [see Clinical Pharmacology (12.4)].

The incidence of major bleeding by renal function status reported in clinical trials of adult patients receiving ARIXTRA for VTE surgical prophylaxis is provided in Table 4. In these patient populations, the following is recommended:

- Do not use ARIXTRA for VTE prophylaxis and treatment in patients with CrCl less than 30 mL/min [see Contraindications (4)].
- ARIXTRA may cause prolonged anticoagulation in patients with CrCl 30 mL/min to 50 mL/min.

Table 4. Incidence of Major Bleeding in Adult Patients Treated with ARIXTRA by Renal Function Status for Surgical Prophylaxis and Treatment of Deep Vein Thrombosis (DVT) and Pulmonary Embolism (PE)
Population | Timing of Dose | Degree of Renal Impairment
Population | Timing of Dose | Normal; %; (n/N) | Mild; %; (n/N) | Moderate; %; (n/N) | Severe; %; (n/N)
CrCl (mL/min) |  | Greater than or equal to 80 | Greater than or equal to 50 to less than 80 | Greater than or equal to 30 to less than 50 | Less than 30
Orthopedic surgery [Hip fracture, hip replacement, and knee replacement surgery prophylaxis.] | Overall | 1.6%; (25/1,565) | 2.4%; (31/1,288) | 3.8%; (19/504) | 4.8%; (4/83)
 | 6 hours to 8 hours after surgery | 1.8%; (16/905) | 2.2%; (15/675) | 2.3%; (6/265) | 0%; (0/40)
Abdominal surgery | Overall | 2.1%; (13/606) | 3.6%; (22/613) | 6.7%; (12/179) | 7.1%; (1/14)
 | 6 hours to 8 hours after surgery | 2.1%; (10/467) | 3.3%; (16/481) | 5.8%; (8/137) | 7.7%; (1/13)
DVT and PE; Treatment |  | 0.4%; (4/1,132) | 1.6%; (12/733) | 2.2%; (7/318) | 7.3%; (4/55)
CrCl = creatinine clearance.

Assess renal function periodically in patients receiving ARIXTRA. Discontinue the drug immediately in patients who develop severe renal impairment while on therapy. After discontinuation of ARIXTRA, its anticoagulant effects may persist for 2 days to 4 days in patients with normal renal function (i.e., at least 3 to 5 half-lives). The anticoagulant effects of ARIXTRA may persist even longer in patients with renal impairment [see Clinical Pharmacology (12.4)].

5.4 Body Weight Less than 50 kg and Bleeding Risk in Adults

ARIXTRA increases the risk for bleeding in adults who weigh less than 50 kg, compared to adults with higher weights.

In adults who weigh less than 50 kg:

- Do not administer ARIXTRA as prophylactic therapy for adults undergoing hip fracture, hip replacement, or knee replacement surgery and abdominal surgery [see Contraindications (4)].

In randomized clinical trials of VTE prophylaxis in adults during the peri-operative period following hip fracture, hip or knee replacement surgery, and abdominal surgery, major bleeding occurred at a higher rate among adults with a body weight less than 50 kg compared to those with a body weight greater than 50 kg (5.4% versus 2.1% in adults undergoing hip fracture, hip replacement, or knee replacement surgery; 5.3% versus 3.3% in adults undergoing abdominal surgery).

5.5 Thrombocytopenia

Thrombocytopenia can occur with the administration of ARIXTRA. Thrombocytopenia of any degree should be monitored closely. Discontinue ARIXTRA if the platelet count falls below 100,000/mm^3. Moderate thrombocytopenia (platelet counts between 100,000/mm^3 and 50,000/mm^3) occurred at a rate of 3% in patients given ARIXTRA 2.5 mg in the peri-operative hip fracture, hip replacement, or knee replacement surgery and abdominal surgery clinical trials. Severe thrombocytopenia (platelet counts less than 50,000/mm^3) occurred at a rate of 0.2% in patients given ARIXTRA 2.5 mg in these clinical trials. During extended prophylaxis, no cases of moderate or severe thrombocytopenia were reported.

Moderate thrombocytopenia occurred at a rate of 0.5% in patients given the ARIXTRA treatment regimen in the DVT and PE treatment clinical trials. Severe thrombocytopenia occurred at a rate of 0.04% in patients given the ARIXTRA treatment regimen in the DVT and PE treatment clinical trials.

Occurrences of thrombocytopenia with thrombosis that manifested similar to heparin-induced thrombocytopenia have been reported with the use of ARIXTRA in postmarketing experience [see Adverse Reactions (6.2)].

5.6 Monitoring: Laboratory Tests

Routine coagulation tests such as Prothrombin Time (PT) and Activated Partial Thromboplastin Time (aPTT) are relatively insensitive measures of the activity of ARIXTRA and international standards of heparin or LMWH are not calibrators to measure anti-Factor Xa activity of ARIXTRA. If unexpected changes in coagulation parameters or major bleeding occur during therapy with ARIXTRA, discontinue ARIXTRA. In postmarketing experience, occurrences of aPTT elevations have been reported following administration of ARIXTRA [see Adverse Reactions (6.2)].

Periodic routine complete blood counts (including platelet count), serum creatinine level, and stool occult blood tests are recommended during the course of treatment with ARIXTRA.

The anti-Factor Xa activity of fondaparinux sodium can be measured by anti-Xa assay using the appropriate calibrator (fondaparinux). The activity of fondaparinux sodium is expressed in milligrams (mg) of the fondaparinux and cannot be compared with activities of heparin or low molecular weight heparins [see Clinical Pharmacology (12.2, 12.3)].

5.7 Latex

The packaging (needle guard) of the prefilled syringe of ARIXTRA contains dry natural latex rubber that may cause allergic reactions in latex sensitive individuals.

6 ADVERSE REACTIONS

The following clinically significant adverse reactions are described elsewhere in the labeling:

- Spinal or epidural hematomas [see Warnings and Precautions (5.1)]
- Hemorrhage [see Warnings and Precautions (5.2)]
- Renal impairment and bleeding risk [see Warnings and Precautions (5.3)]
- Body weight less than 50 kg and bleeding risk [see Warnings and Precautions (5.4)]
- Thrombocytopenia [see Warnings and Precautions (5.5)]

6.1 Clinical Trials Experience

Because clinical trials are conducted under widely varying conditions, adverse reaction rates observed in the clinical trials of a drug cannot be directly compared to rates in the clinical trials of another drug and may not reflect the rates observed in practice.

Clinical Trials Experience in Adults

The adverse reaction information below is based on data from 8,877 patients exposed to ARIXTRA in controlled trials of hip fracture, hip replacement, major knee, or abdominal surgeries, and DVT and PE treatment.

Hemorrhage

During administration of ARIXTRA, the most common adverse reactions were bleeding complications [see Warnings and Precautions (5.2)].

Hip Fracture, Hip Replacement, and Knee Replacement Surgery

The rates of major bleeding events reported during 3 active-controlled peri-operative VTE prophylaxis trials with enoxaparin sodium in hip fracture, hip replacement, or knee replacement surgery (N = 3,616) and in an extended VTE prophylaxis trial (n = 327) with ARIXTRA 2.5 mg are provided in Table 5.

Table 5. Bleeding Across Randomized, Controlled Hip Fracture, Hip Replacement, and Knee Replacement Surgery Studies
 | Peri-Operative Prophylaxis (Day 1 to Day 7 ± 1 post-surgery) |  | Extended Prophylaxis (Day 8 to Day 28 ± 2 post-surgery)
 | ARIXTRA; 2.5 mg subcutaneously; once daily; N = 3,616 | Enoxaparin Sodium [Enoxaparin sodium dosing regimen: 30 mg every 12 hours or 40 mg once daily.] , [Not approved for use in patients undergoing hip fracture surgery.]; N = 3,956 | ARIXTRA; 2.5 mg subcutaneously; once daily; N = 327 | Placebo subcutaneously; once daily; N = 329
Major bleeding [Major bleeding was defined as clinically overt bleeding that was (1) fatal, (2) bleeding at critical site (e.g., intracranial, retroperitoneal, intraocular, pericardial, spinal, or into adrenal gland), (3) associated with re-operation at operative site, or (4) with a bleeding index (BI) greater than or equal to 2.] | 96 (2.7%) | 75 (1.9%) | 8 (2.4%) | 2 (0.6%)
Hip fracture | 18/831 (2.2%) | 19/842 (2.3%) | 8/327 (2.4%) | 2/329 (0.6%)
Hip replacement | 67/2,268 (3.0%) | 55/2,597 (2.1%) | — | —
Knee replacement | 11/517 (2.1%) | 1/517 (0.2%) | — | —
Fatal bleeding | 0 (0%) | 1 (less than 0.1%) | 0 (0%) | 0 (0%)
Non-fatal bleeding at critical site | 0 (0%) | 1 (less than 0.1%) | 0 (0%) | 0 (0%)
Re-operation due to bleeding | 12 (0.3%) | 10 (0.3%) | 2 (0.6%) | 2 (0.6%)
BI greater than or equal to 2 [BI greater than or equal to 2: Overt bleeding associated only with a bleeding index (BI) greater than or equal to 2 calculated as [number of whole blood or packed red blood cell units transfused + [(pre-bleeding) – (post-bleeding)] hemoglobin (g/dL) values].] | 84 (2.3%) | 63 (1.6%) | 6 (1.8%) | 0 (0%)
Minor bleeding [Minor bleeding was defined as clinically overt bleeding that was not major.] | 109 (3%) | 116 (2.9%) | 5 (1.5%) | 2 (0.6%)

A separate analysis of major bleeding across all randomized, controlled, peri-operative, prophylaxis clinical studies of hip fracture, hip replacement, or knee replacement surgery according to the time of the first injection of ARIXTRA after surgical closure was performed in patients who received ARIXTRA only post-operatively. In this analysis, the incidences of major bleeding were as follows: less than 4 hours was 4.8% (5/104), 4 to 6 hours was 2.3% (28/1,196), 6 to 8 hours was 1.9% (38/1,965). In all studies, the majority (greater than or equal to 75%) of the major bleeding events occurred during the first 4 days after surgery.

Abdominal Surgery

In a randomized study of patients undergoing abdominal surgery, ARIXTRA 2.5 mg once daily (n = 1,433) was compared with dalteparin 5,000 IU once daily (n = 1,425). Bleeding rates are shown in Table 6.

Table 6. Bleeding in the Abdominal Surgery Study
 | ARIXTRA; 2.5 mg subcutaneously once daily | Dalteparin Sodium; 5,000 IU subcutaneously once daily
 | N = 1,433 | N = 1,425
Major bleeding [Major bleeding was defined as bleeding that was (1) fatal, (2) bleeding at the surgical site leading to intervention, (3) non-surgical bleeding at a critical site (e.g. intracranial, retroperitoneal, intraocular, pericardial, spinal, or into adrenal gland), or leading to an intervention, and/or with a bleeding index (BI) greater than or equal to 2.] | 49 (3.4%) | 34 (2.4%)
Fatal bleeding | 2 (0.1%) | 2 (0.1%)
Non-fatal bleeding at critical site | 0 (0%) | 0 (0%)
Other non-fatal major bleeding
Surgical site | 38 (2.7%) | 26 (1.8%)
Non-surgical site | 9 (0.6%) | 6 (0.4%)
Minor bleeding [Minor bleeding was defined as clinically overt bleeding that was not major.] | 31 (2.2%) | 23 (1.6%)

The rates of major bleeding according to the time interval following the first ARIXTRA injection were as follows: less than 6 hours was 3.4% (9/263) and 6 hours to 8 hours was 2.9% (32/1,112).

Treatment of Deep Vein Thrombosis and Pulmonary Embolism

The rates of bleeding events reported during a dose-response trial (n = 111) and an active-controlled trial with enoxaparin sodium in DVT treatment (n = 1,091) and an active-controlled trial with heparin in PE treatment (n = 1,092) with ARIXTRA are provided in Table 7.

Table 7. Bleeding [Bleeding rates are during the study drug treatment period (approximately 7 days). Patients were also treated with vitamin K antagonists initiated within 72 hours after the first study drug administration.] in Deep Vein Thrombosis and Pulmonary Embolism Treatment Studies
 | ARIXTRA; N = 2,294 | Enoxaparin Sodium; N = 1,101 | Heparin; aPTT adjusted IV; N = 1,092
Major bleeding [Major bleeding was defined as clinically overt: – and/or contributing to death – and/or in a critical organ including intracranial, retroperitoneal, intraocular, spinal, pericardial, or adrenal gland – and/or associated with a fall in hemoglobin level greater than or equal to 2 g/dL – and/or leading to a transfusion greater than or equal to 2 units of packed red blood cells or whole blood.] | 28 (1.2%) | 13 (1.2%) | 12 (1.1%)
Fatal bleeding | 3 (0.1%) | 0 (0%) | 1 (0.1%)
Non-fatal bleeding at a critical site | 3 (0.1%) | 0 (0%) | 2 (0.2%)
Intracranial bleeding | 3 (0.1%) | 0 (0%) | 1 (0.1%)
Retro-peritoneal bleeding | 0 (0%) | 0 (0%) | 1 (0.1%)
Other clinically overt bleeding [Clinically overt bleeding with a 2 g/dL fall in hemoglobin and/or leading to transfusion of PRBC or whole blood greater than or equal to 2 units.] | 22 (1%) | 13 (1.2%) | 10 (0.9%)
Minor bleeding [Minor bleeding was defined as clinically overt bleeding that was not major.] | 70 (3.1%) | 33 (3%) | 57 (5.2%)

Local Reactions

Local irritation (injection site bleeding, rash, and pruritus) has occurred following subcutaneous injection of ARIXTRA.

Elevations of Serum Aminotransferases

In the peri-operative prophylaxis randomized clinical trials of 7 ± 2 days, asymptomatic increases in aspartate (AST) and alanine (ALT) aminotransferase levels greater than 3 times the upper limit of normal were reported in 1.7% and 2.6% of patients, respectively, during treatment with ARIXTRA 2.5 mg once daily versus 3.2% and 3.9% of patients, respectively, during treatment with enoxaparin sodium 30 mg every 12 hours or 40 mg once daily enoxaparin sodium. These elevations are reversible and may be associated with increases in bilirubin. In the extended prophylaxis clinical trial, no significant differences in AST and ALT levels between ARIXTRA 2.5 mg and placebo-treated patients were observed.

In the DVT and PE treatment clinical trials, asymptomatic increases in AST and ALT levels greater than 3 times the upper limit of normal of the laboratory reference range were reported in 0.7% and 1.3% of patients, respectively, during treatment with ARIXTRA. In comparison, these increases were reported in 4.8% and 12.3% of patients, respectively, in the DVT treatment trial during treatment with enoxaparin sodium 1 mg/kg every 12 hours and in 2.9% and 8.7% of patients, respectively, in the PE treatment trial during treatment with aPTT adjusted heparin.

Since aminotransferase determinations are important in the differential diagnosis of myocardial infarction, liver disease, and pulmonary emboli, elevations that might be caused by drugs like ARIXTRA should be interpreted with caution.

Other adverse reactions that occurred during treatment with ARIXTRA in clinical trials with patients undergoing hip fracture, hip replacement, or knee replacement surgery are provided in Table 8.

Table 8. Adverse Reactions Across Randomized, Controlled, Hip Fracture Surgery, Hip Replacement Surgery, and Knee Replacement Surgery Studies
Adverse Reactions | Peri-Operative Prophylaxis; (Day 1 to Day 7 ± 1 post-surgery) |  | Extended Prophylaxis; (Day 8 to Day 28 ± 2 post-surgery)
Adverse Reactions | ARIXTRA; 2.5 mg subcutaneously; once daily | Enoxaparin Sodium [Enoxaparin sodium dosing regimen: 30 mg every 12 hours or 40 mg once daily.] , [Not approved for use in patients undergoing hip fracture surgery.] | ARIXTRA; 2.5 mg subcutaneously; once daily | Placebo subcutaneously once daily
 | N = 3,616 | N = 3,956 | N = 327 | N = 329
Anemia | 707 (19.6%) | 670 (16.9%) | 5 (1.5%) | 4 (1.2%)
Insomnia | 179 (5%) | 214 (5.4%) | 3 (0.9%) | 1 (0.3%)
Wound drainage increased | 161 (4.5%) | 184 (4.7%) | 2 (0.6%) | 0 (0%)
Hypokalemia | 152 (4.2%) | 164 (4.1%) | 0 (0%) | 0 (0%)
Dizziness | 131 (3.6%) | 165 (4.2%) | 2 (0.6%) | 0 (0%)
Purpura | 128 (3.5%) | 137 (3.5%) | 0 (0%) | 0 (0%)
Hypotension | 126 (3.5%) | 125 (3.2%) | 1 (0.3%) | 0 (0%)
Confusion | 113 (3.1%) | 132 (3.3%) | 4 (1.2%) | 1 (0.3%)
Bullous eruption [Localized blister coded as bullous eruption.] | 112 (3.1%) | 102 (2.6%) | 0 (0%) | 1 (0.3%)
Hematoma | 103 (2.8%) | 109 (2.8%) | 7 (2.1%) | 1 (0.3%)
Post-operative hemorrhage | 85 (2.4%) | 69 (1.7%) | 2 (0.6%) | 2 (0.6%)

The most common adverse reaction in the abdominal surgery trial was post-operative wound infection (4.9%), and the most common adverse reaction in the VTE treatment trials was epistaxis (1.3%).

Clinical Trials Experience in Pediatric Patients

Safety data for use of ARIXTRA in the treatment of VTE in pediatric patients aged 1 year or older is available from Study FDPX-IJS-7001. In Study FDPX-IJS-7001 (n = 366), the median duration of treatment with fondaparinux sodium injection, including ARIXTRA, was 85 days (range 1 day to 3,768 days).

The incidence of major bleeding events, defined as per the ISTH criteria, was the primary safety outcome of interest in Study FDPX-IJS-7001. Seven patients (1.9%) had composite major bleeding events: 1 patient (0.3%) had clinically overt bleeding (associated with a decrease in hemoglobin of at least 20 g/L (2 g/dL) in a 24-hour period), 3 patients (0.8%) had bleeding that was retroperitoneal, pulmonary, intracranial, or otherwise involved the central nervous system, and 3 patients (0.8%) had major bleeding that required surgical intervention in an operating suite. Major bleeding events resulted in the interruption of fondaparinux sodium injection treatment for 4 patients and the discontinuation of fondaparinux sodium injection for 3 patients. All major bleeding events were reported in patients between the ages of greater than or equal to 2 years to less than 18 years.

Eleven patients (3%) had non-major bleeding events: 8 patients (2.2%) had overt bleeding for which a blood product was administered, and which was not directly attributable to the patient’s underlying medical condition and 4 patients (1.1%) had bleeding that required medical or surgical intervention to restore hemostasis other than in an operating room. All non-major bleeding events warranted either interruption or withdrawal of fondaparinux sodium injection treatment except for 1 patient for whom the action taken with fondaparinux was not reported. All non-major bleeding events were reported in patients between the ages of greater than or equal to 2 years to less than 18 years.

Overall, 65 patients (18%) had composite minor bleeding events: 64 patients (18%) had overt or macroscopic evidence of bleeding that did not fulfill the criteria for either major bleeding or clinically relevant, non-major bleeding and two patients (0.5%) had non-major menstrual bleeding which resulted in a medical consultation and/or intervention.

Other adverse reactions that occurred during treatment with fondaparinux sodium injection in pediatric studies included: anemia, thrombocytopenia, allergic reactions, generalized skin associated events, abnormal liver function, hypokalemia, and hypotension.

6.2 Postmarketing Experience

The following adverse reactions have been identified during post-approval use of ARIXTRA. Because these reactions are reported voluntarily from a population of uncertain size, it is not always possible to reliably estimate their frequency or establish a causal relationship to drug exposure.

In the postmarketing experience, epidural or spinal hematoma has been reported in association with the use of ARIXTRA by subcutaneous (SC) injection [see Warnings and Precautions (5.1)]. Occurrences of thrombocytopenia with thrombosis that manifested similar to heparin-induced thrombocytopenia have been reported in the postmarketing experience and cases of elevated aPTT temporally associated with bleeding events have been reported following administration of ARIXTRA (with or without concomitant administration of other anticoagulants) [see Warnings and Precautions (5.5)].

Serious allergic reactions, including angioedema, anaphylactoid/anaphylactic reactions have been reported with the use of ARIXTRA [see Contraindications (4)].

Elevations of hepatic transaminases have been reported in pediatric patients with elevations greater than 10x ULN.

7 DRUG INTERACTIONS

In clinical studies performed with ARIXTRA, the concomitant use of oral anticoagulants (warfarin sodium), platelet inhibitors (acetylsalicylic acid), NSAIDs (piroxicam), and digoxin did not significantly affect the pharmacokinetics/pharmacodynamics of fondaparinux sodium. In addition, ARIXTRA neither influenced the pharmacodynamics of warfarin sodium, acetylsalicylic acid, piroxicam, and digoxin, nor the pharmacokinetics of digoxin at steady state.

Agents that may enhance the risk of hemorrhage should be discontinued prior to initiation of therapy with ARIXTRA unless these agents are essential. If co-administration is necessary, monitor patients closely for hemorrhage [see Warnings and Precautions (5.2)].

In an in vitro study in human liver microsomes, inhibition of CYP2A6 hydroxylation of coumarin by fondaparinux (200 micromolar i.e., 350 mg/L) was 17% to 28%. Inhibition of the other isozymes evaluated (CYPs 1A2, 2C9, 2C19, 2D6, 3A4, and 3E1) was 0% to 16%. Since fondaparinux does not markedly inhibit CYP450s (CYP1A2, CYP2A6, CYP2C9, CYP2C19, CYP2D6, CYP2E1, or CYP3A4) in vitro, fondaparinux sodium is not expected to significantly interact with other drugs in vivo by inhibition of metabolism mediated by these isozymes.

Since fondaparinux sodium does not bind significantly to plasma proteins other than ATIII, no drug interactions by protein-binding displacement are expected.

8 USE IN SPECIFIC POPULATIONS

8.1 Pregnancy

Risk Summary

Available data from published literature and postmarketing reports have not reported a clear association with fondaparinux sodium and adverse developmental outcomes. Fondaparinux sodium plasma concentrations obtained from four women treated with ARIXTRA during pregnancy and their newborn infants demonstrated low placental transfer of fondaparinux sodium (see Data). There are risks to the mother associated with untreated venous thromboembolism in pregnancy and a risk of hemorrhage in the mother and fetus associated with use of anticoagulants (see Clinical Considerations). In animal reproduction studies, there was no evidence of adverse developmental outcomes when fondaparinux sodium was administered to pregnant rats and rabbits during organogenesis at doses 32 times and 65 times, respectively, the recommended human dose based on body surface area.

The estimated background risk of major birth defects and miscarriage for the indicated population is unknown. All pregnancies have a background risk of birth defect, loss, or other adverse outcomes. In the U.S. general population, the estimated background risk of major birth defects and miscarriage in clinically recognized pregnancies is 2% to 4% and 15% to 20%, respectively.

Clinical Considerations

Disease-Associated Maternal and/or Embryo/Fetal Risk

Pregnancy confers an increased risk for thromboembolism that is higher for women with underlying thromboembolic disease and certain high-risk pregnancy conditions. Published data describe that women with a previous history of venous thrombosis are at high risk for recurrence during pregnancy.

Fetal/Neonatal Adverse Reactions

Fondaparinux sodium has been demonstrated to cross the placenta in humans (see Data). Use of anticoagulants, including fondaparinux sodium, may increase the risk of bleeding in the fetus and neonate. Monitor neonates for bleeding [see Warnings and Precautions (5.2, 5.4, 5.6)].

Labor or Delivery

All patients receiving anticoagulants, including pregnant women, are at risk for bleeding. Fondaparinux sodium use during labor or delivery in women who are receiving neuraxial anesthesia may result in epidural or spinal hematomas. Pregnant women receiving fondaparinux sodium should be carefully monitored for evidence of bleeding or unexpected changes in coagulation parameters. Consideration for use of a shorter acting anticoagulant should be specifically addressed as delivery approaches [see Warnings and Precautions (5.1, 5.6)].

Data

Human Data

In a study of five pregnant women treated with fondaparinux sodium during the third trimester of pregnancy at a dose of 2.5 mg/day, four of the women had elevated anti-factor Xa activity noted in the cord blood. Anti-factor Xa clotting times in these four cases were between 37.5 seconds and 50.9 seconds. The patient who did not have elevated anti-factor Xa activity had received only one dose of fondaparinux sodium 22 hours prior to delivery. The concentration of fondaparinux sodium in umbilical cord plasma was approximately 1/10th the level of fondaparinux sodium in maternal plasma. None of the infants experienced adverse effects.

Animal Data

Embryo-fetal development studies have been conducted with fondaparinux sodium in pregnant rats at subcutaneous doses up to 10 mg/kg/day (about 32 times the recommended human dose based on body surface area) administered from days 6 to 17 of gestation and pregnant rabbits at subcutaneous doses up to 10 mg/kg/day (about 65 times the recommended human dose based on body surface area) administered from days 6 to 18 of gestation. These studies have revealed no evidence of adverse developmental outcomes when fondaparinux sodium was administered to pregnant rats and rabbits during organogenesis. Additionally, there were no effects on pre- and postnatal development in a study conducted in rats at subcutaneous doses up to 10 mg/kg/day (about 32 times the recommended human dose based on body surface area).

8.2 Lactation

Risk Summary

There are no data on the presence of fondaparinux sodium in human milk, or the effects on milk production. Limited clinical data during lactation preclude a clear determination of the risk of ARIXTRA to an infant during lactation; therefore, the developmental and health benefits of breastfeeding should be considered along with the mother’s clinical need for ARIXTRA and any potential adverse effects on the breastfed infant from ARIXTRA or from the underlying maternal condition.

8.4 Pediatric Use

The safety and effectiveness of ARIXTRA for the treatment of venous thromboembolism have been established in pediatric patients aged 1 year and older weighing at least 10 kg. Use of ARIXTRA for this indication is supported by evidence from adequate and well-controlled studies in adults with additional pharmacokinetic, pharmacodynamic, safety, and efficacy data in pediatric patients aged 0.3 years and older [see Adverse Reactions (6.1), Clinical Pharmacology (12.4), and Clinical Studies (14.8)]. The frequency, type, and severity of adverse reactions observed were generally consistent with those observed in adults.

The safety and effectiveness of ARIXTRA have not been established in pediatric patients for the treatment of venous thromboembolism who are younger than 1 year old, weigh less than 10 kg, or with any category of renal or hepatic impairment.

The safety and effectiveness of ARIXTRA have not been established in pediatric patients for the prophylaxis of DVT and treatment of DVT or PE in conjunction with warfarin sodium.

8.5 Geriatric Use

Over 3,000 patients 65 years and older have received ARIXTRA in randomized clinical trials for the treatment or prophylaxis of DVT and PE. There were over 2,000 patients 65 years of age and older in the orthopedic surgery clinical studies for prophylaxis of DVT and PE [see Clinical Studies (14)]. Of the total number of ARIXTRA-treated patients in these orthopedic surgery studies, 1,111 (30.9%) were 65 years of age to 74 years of age, while 1,227 (34.2%) were 75 years of age and older. No overall differences in effectiveness of ARIXTRA have been observed between patients 65 years of age and older and younger adult patients. Serious adverse events were more frequent in patients 65 years of age and older. When using ARIXTRA in elderly patients, pay particular attention to dosing directions and concomitant medications (especially anti-platelet medication) [see Warnings and Precautions (5.2)].

Fondaparinux sodium is substantially excreted by the kidney, and the risk of adverse reactions to ARIXTRA may be greater in patients with impaired renal function. Because geriatric patients are more likely to have decreased renal function, assess renal function prior to ARIXTRA administration [see Contraindications (4), Warnings and Precautions (5.3), and Clinical Pharmacology (12.4)].

In the peri-operative hip fracture, hip replacement, or knee replacement surgery clinical trials with patients receiving ARIXTRA 2.5 mg, serious adverse events increased with age for patients receiving ARIXTRA. The incidence of major bleeding in clinical trials of ARIXTRA by age is provided in Table 9.

Table 9. Incidence of Major Bleeding in Patients Treated with ARIXTRA by Age
 | Age
 | Less than 65 years; % (n/N) | 65 years to 74 years; % (n/N) | Greater than or equal to 75 years; % (n/N)
Orthopedic surgery [Includes hip fracture, hip replacement, and knee replacement surgery prophylaxis.] | 1.8% (23/1,253) | 2.2% (24/1,111) | 2.7% (33/1,277)
Extended prophylaxis | 1.9% (1/52) | 1.4% (1/71) | 2.9% (6/204)
Abdominal surgery | 3% (19/644) | 3.2% (16/507) | 5% (14/282)
DVT and PE treatment | 0.6% (7/1,151) | 1.6% (9/560) | 2.1% (12/583)

8.6 Renal Impairment

Patients with impaired renal function are at increased risk of bleeding due to reduced clearance of ARIXTRA [see Contraindications (4) and Warnings and Precautions (5.3)]. Assess renal function periodically in patients receiving ARIXTRA. Discontinue ARIXTRA immediately in patients who develop severe renal impairment while on therapy. After discontinuation of ARIXTRA, its anticoagulant effects may persist for 2 days to 4 days in patients with normal renal function (i.e., at least 3 to 5 half-lives). The anticoagulant effects of ARIXTRA may persist even longer in patients with renal impairment [see Clinical Pharmacology (12.4)].

There is no adequate data to support safe and effective use of ARIXTRA in pediatric patients with renal impairment.

8.7 Hepatic Impairment

Following a single, subcutaneous dose of 7.5 mg of ARIXTRA in patients with moderate hepatic impairment (Child-Pugh Category B) compared to subjects with normal liver function, changes from baseline in aPTT, PT/INR, and antithrombin III were similar in the two groups. However, a higher incidence of hemorrhage was observed in subjects with moderate hepatic impairment than in normal subjects, especially mild hematomas at the blood sampling or injection site. The pharmacokinetics of fondaparinux have not been studied in patients with severe hepatic impairment [see Dosage and Administration (2.6) and Clinical Pharmacology (12.4)]. There is no adequate data to support safe and effective use of ARIXTRA in pediatric patients with hepatic impairment.

10 OVERDOSAGE

Overdose of ARIXTRA may lead to hemorrhagic complications. Discontinue treatment and initiate appropriate therapy if bleeding complications associated with overdosage occur. There is no known antidote for ARIXTRA.

Data obtained in patients undergoing chronic intermittent hemodialysis suggest that clearance of ARIXTRA can increase by 20% during hemodialysis.

11 DESCRIPTION

ARIXTRA (fondaparinux sodium injection, USP) is a sterile solution containing fondaparinux sodium. It is a synthetic and specific inhibitor of activated Factor X (Xa). Fondaparinux sodium is methyl O-2-deoxy-6-O-sulfo-2-(sulfoamino)-α-D-glucopyranosyl-(1→4)-O-β-D-glucopyra-nuronosyl-(1→4)-O-2-deoxy-3,6-di-O-sulfo-2-(sulfoamino)-α-D-glucopyranosyl-(1→4)-O-2-O-sulfo-α-L-idopyranuronosyl-(1→4)-2-deoxy-6-O-sulfo-2-(sulfoamino)-α-D-glucopyranoside, decasodium salt.

The molecular formula of fondaparinux sodium is C31H43N3Na10O49S8 and its molecular weight is 1728. The structural formula is provided below:

ARIXTRA is supplied as a sterile, preservative-free injectable solution for subcutaneous use.

Each single-dose, prefilled syringe of ARIXTRA, affixed with an automatic needle protection system, contains 2.5 mg of fondaparinux sodium in 0.5 mL, 5 mg of fondaparinux sodium in 0.4 mL, 7.5 mg of fondaparinux sodium in 0.6 mL, or 10 mg of fondaparinux sodium in 0.8 mL of an isotonic solution of sodium chloride and water for injection. May also contain sodium hydroxide and/or hydrochloric acid as pH adjusters. The final drug product is a clear and colorless to slightly yellow liquid with a pH between 5 and 8.

12 CLINICAL PHARMACOLOGY

12.1 Mechanism of Action

The antithrombotic activity of fondaparinux sodium is the result of antithrombin III (ATIII)-mediated selective inhibition of Factor Xa. By selectively binding to ATIII, fondaparinux sodium potentiates (about 300 times) the innate neutralization of Factor Xa by ATIII. Neutralization of Factor Xa interrupts the blood coagulation cascade and thus inhibits thrombin formation and thrombus development.

Fondaparinux sodium does not inactivate thrombin (activated Factor II) and has no known effect on platelet function. At the recommended dose, fondaparinux sodium does not affect fibrinolytic activity or bleeding time.

12.2 Pharmacodynamics

Anti-Xa Activity

The pharmacodynamics/pharmacokinetics of fondaparinux sodium are derived from fondaparinux plasma concentrations quantified via anti-Factor Xa activity. Only fondaparinux can be used to calibrate the anti-Xa assay. (The international standards of heparin or LMWH are not appropriate for this use.) As a result, the activity of fondaparinux sodium is expressed as milligrams (mg) of the fondaparinux calibrator. The anti-Xa activity of the drug increases with increasing drug concentration, reaching maximum values in approximately three hours.

12.3 Pharmacokinetics

Absorption

Fondaparinux sodium administered by subcutaneous injection is rapidly and completely absorbed (absolute bioavailability is 100%). Following a single subcutaneous dose of fondaparinux sodium 2.5 mg in young male subjects, Cmax of 0.34 mg/L is reached in approximately 2 hours. In patients undergoing treatment with fondaparinux sodium injection 2.5 mg, once daily, the peak steady-state plasma concentration is, on average, 0.39 mg/L to 0.5 mg/L and is reached approximately 3 hours post-dose. In these patients, the minimum steady-state plasma concentration is 0.14 mg/L to 0.19 mg/L. In patients with symptomatic deep vein thrombosis and pulmonary embolism undergoing treatment with fondaparinux sodium injection 5 mg (body weight less than 50 kg), 7.5 mg (body weight 50 kg to 100 kg), and 10 mg (body weight greater than 100 kg) once daily, the body-weight-adjusted doses provide similar mean steady-state peaks and minimum plasma concentrations across all body weight categories. The mean peak steady-state plasma concentration is in the range of 1.20 mg/L to 1.26 mg/L. In these patients, the mean minimum steady-state plasma concentration is in the range of 0.46 mg/L to 0.62 mg/L.

Distribution

In healthy adults, intravenously or subcutaneously administered fondaparinux sodium distributes mainly in blood and only to a minor extent in extravascular fluid as evidenced by steady state and non-steady state apparent volume of distribution of 7 L to 11 L. Similar fondaparinux distribution occurs in patients undergoing elective hip surgery or hip fracture surgery. In vitro, fondaparinux sodium is highly (at least 94%) and specifically bound to antithrombin III (ATIII) and does not bind significantly to other plasma proteins (including platelet Factor 4 [PF4]) or red blood cells.

Metabolism

In vivo metabolism of fondaparinux has not been investigated since the majority of the administered dose is eliminated unchanged in urine in individuals with normal kidney function.

Elimination

In individuals with normal kidney function, fondaparinux is eliminated in urine mainly as unchanged drug. In healthy individuals up to 75 years of age, up to 77% of a single subcutaneous or intravenous fondaparinux dose is eliminated in urine as unchanged drug in 72 hours. The elimination half-life is 17 hours to 21 hours.

12.4 Special Populations

Renal Impairment

Fondaparinux elimination is prolonged in patients with renal impairment since the major route of elimination is urinary excretion of unchanged drug. In patients undergoing prophylaxis following elective hip surgery or hip fracture surgery, the total clearance of fondaparinux is approximately 25% lower in patients with mild renal impairment (CrCl 50 mL/min to 80 mL/min), approximately 40% lower in patients with moderate renal impairment (CrCl 30 mL/min to 50 mL/min), and approximately 55% lower in patients with severe renal impairment (less than 30 mL/min) compared to patients with normal renal function. A similar relationship between fondaparinux clearance and extent of renal impairment was observed in DVT treatment patients [see Contraindications (4) and Warnings and Precautions (5.3)].

Hepatic Impairment

Following a single, subcutaneous dose of 7.5 mg of ARIXTRA in patients with moderate hepatic impairment (Child-Pugh Category B), Cmax and AUC were decreased by 22% and 39%, respectively, compared to subjects with normal liver function. The changes from baseline in pharmacodynamic parameters, such as aPTT, PT/INR, and antithrombin III, were similar in normal subjects and in patients with moderate hepatic impairment. Based on these data, no dosage adjustment is recommended in these patients. However, a higher incidence of hemorrhage was observed in subjects with moderate hepatic impairment than in normal subjects [see Use in Specific Populations (8.7)]. The pharmacokinetics of fondaparinux have not been studied in patients with severe hepatic impairment [see Dosage and Administration (2.6)].

Pediatric

Study FDPX-IJS-7001 characterized the fondaparinux peak level of once-daily subcutaneous fondaparinux sodium injection in 336 pediatric patients by measuring anti-Factor Xa activity. Of these patients, 93% achieved a therapeutic blood concentration of fondaparinux (0.5 mg/L to 1 mg/L) during the course of their treatment following the recommended dose adjustments, as necessary. The median time to reach therapeutic levels across all age groups was approximately 3 days, with an interquartile range of 2 days to 6 days. Less than 3% of patients remained in subtherapeutic levels and 5% of patients remained in supratherapeutic levels during the course of their treatment. Approximately 55% of patients did not require any dose adjustment to reach a therapeutic blood concentration of fondaparinux during the course of their treatment; nearly 20% required one dose adjustment, 11% required 2 dose adjustments, and approximately 10% required more than two dose adjustments during the course of treatment to reach therapeutic concentrations of fondaparinux [see Contraindications (4), Warnings and Precautions (5.4), and Use in Specific Populations (8.4)].

Geriatric

Fondaparinux elimination is prolonged in patients older than 75 years. In studies evaluating fondaparinux sodium 2.5 mg prophylaxis in hip fracture surgery or elective hip surgery, the total clearance of fondaparinux was approximately 25% lower in patients older than 75 years as compared to patients younger than 65 years. A similar relationship between fondaparinux clearance and age was observed in DVT treatment patients [see Use in Specific Populations (8.5)].

Patients Weighing Less than 50 kg

Total clearance of fondaparinux sodium is decreased by approximately 30% in patients weighing less than 50 kg [see Dosage and Administration (2.4) and Contraindications (4)].

Gender

The pharmacokinetic properties of fondaparinux sodium are not significantly affected by gender.

Race

Pharmacokinetic differences due to race have not been studied prospectively. However, studies performed in Asian (Japanese) healthy subjects did not reveal a different pharmacokinetic profile compared to Caucasian healthy subjects. Similarly, no plasma clearance differences were observed between black and Caucasian patients undergoing orthopedic surgery.

13 NONCLINICAL TOXICOLOGY

13.1 Carcinogenesis, Mutagenesis, Impairment of Fertility

No long-term studies in animals have been performed to evaluate the carcinogenic potential of fondaparinux sodium.

Fondaparinux sodium was not genotoxic in the Ames test, the mouse lymphoma cell (L5178Y/TK+/-) forward mutation test, the human lymphocyte chromosome aberration test, the rat hepatocyte unscheduled DNA synthesis (UDS) test, or the rat micronucleus test.

At subcutaneous doses up to 10 mg/kg/day (about 32 times the recommended human dose based on body surface area), fondaparinux sodium was found to have no effect on fertility and reproductive performance of male and female rats.

14 CLINICAL STUDIES

14.1 Prophylaxis of Thromboembolic Events Following Hip Fracture Surgery in Adult Patients

In a randomized, double-blind, clinical trial in patients undergoing hip fracture surgery, ARIXTRA 2.5 mg subcutaneously once daily was compared to enoxaparin sodium 40 mg subcutaneously once daily, which is not approved for use in patients undergoing hip fracture surgery. A total of 1,711 patients were randomized and 1,673 were treated. Patients ranged in age from 17 years to 101 years (mean age 77 years) with 25% men and 75% women. Patients were 99% Caucasian, 1% other races. Patients with multiple traumas affecting more than one organ system, serum creatinine level more than 2 mg/dL (180 micromol/L), or platelet count less than 100,000/mm^3 were excluded from the trial. ARIXTRA was initiated after surgery in 88% of patients (mean 6 hours) and enoxaparin sodium was initiated after surgery in 74% of patients (mean 18 hours). For both drugs, treatment was continued for 7 ± 2 days. The primary efficacy endpoint, venous thromboembolism (VTE), was a composite of documented deep vein thrombosis (DVT) and/or documented symptomatic pulmonary embolism (PE) reported up to Day 11. The efficacy data are provided in Table 10 and demonstrate that under the conditions of the trial ARIXTRA was associated with a VTE rate of 8.3% compared with a VTE rate of 19.1% for enoxaparin sodium for a relative risk reduction of 56% (95% CI: 39%, 70%; P <0.001). Major bleeding episodes occurred in 2.2% of patients receiving ARIXTRA and 2.3% of enoxaparin sodium patients [see Adverse Reactions (6.1)].

Table 10. Efficacy of ARIXTRA in the Peri-operative Prophylaxis of Thromboembolic Events Following Hip Fracture Surgery
Endpoint | Peri-operative Prophylaxis; (Day 1 to Day 7 ± 2 post-surgery)
Endpoint | ARIXTRA; 2.5 mg subcutaneously once daily |  | Enoxaparin Sodium; 40 mg subcutaneously once daily
 | n/N [N = all evaluable hip fracture surgery patients. Evaluable patients were those who were treated and underwent the appropriate surgery (i.e., hip fracture surgery of the upper third of the femur), with an adequate efficacy assessment up to Day 11.] | % (95% CI) | n/N | % (95% CI)
VTE | 52/626 | 8.3% [P value versus enoxaparin sodium <0.001.] (6.3, 10.8) | 119/624 | 19.1% (16.1, 22.4)
All DVT | 49/624 | 7.9% (5.9, 10.2) | 117/623 | 18.8% (15.8, 22.1)
Proximal DVT | 6/650 | 0.9% (0.3, 2) | 28/646 | 4.3% (2.9, 6.2)
Symptomatic PE | 3/831 | 0.4% [P value versus enoxaparin sodium: NS.] (0.1, 1.1) | 3/840 | 0.4% (0.1, 1)

14.2 Extended Prophylaxis of Thromboembolic Events Following Hip Fracture Surgery in Adult Patients

In a noncomparative, unblinded manner, 737 patients undergoing hip fracture surgery were initially treated during the peri-operative period with ARIXTRA 2.5 mg once daily for 7 ± 1 days. Eighty-one (81) of the 737 patients were not eligible for randomization into the 3-week double-blind period. Three hundred twenty-six (326) patients and 330 patients were randomized to receive ARIXTRA 2.5 mg once daily or placebo, respectively, in or out of the hospital for 21 ± 2 days. Patients ranged in age from 23 years to 96 years (mean age 75 years) and were 29% men and 71% women. Patients were 99% Caucasian and 1% other races. Patients with multiple traumas affecting more than one organ system or serum creatinine level more than 2 mg/dL (180 micromol/L) were excluded from the trial. The primary efficacy endpoint, venous thromboembolism (VTE), was a composite of documented deep vein thrombosis (DVT) and/or documented symptomatic pulmonary embolism (PE) reported for up to 24 days following randomization. The efficacy data are provided in Table 11 and demonstrate that extended prophylaxis with ARIXTRA was associated with a VTE rate of 1.4% compared with a VTE rate of 35% for placebo for a relative risk reduction of 95.9% (95% CI = [98.7; 87.1], P <0.0001). Major bleeding rates during the 3-week extended prophylaxis period for ARIXTRA occurred in 2.4% of patients receiving ARIXTRA and 0.6% of placebo-treated patients [see Adverse Reactions (6.1)].

Table 11. Efficacy of ARIXTRA Injection in the Extended Prophylaxis of Thromboembolic Events Following Hip Fracture Surgery
Endpoint | Extended Prophylaxis; (Day 8 to Day 28 ± 2 post-surgery)
Endpoint | ARIXTRA; 2.5 mg subcutaneously; once daily |  | Placebo; subcutaneously; once daily
 | n/N [N = all randomized evaluable hip fracture surgery patients. Evaluable patients were those who were treated in the post-randomization period, with an adequate efficacy assessment for up to 24 days following randomization.] | % (95% CI) | n/N | % (95% CI)
VTE | 3/208 | 1.4% [P value versus placebo <0.001] (0.3, 4.2) | 77/220 | 35% (28.7, 41.7)
All DVT | 3/208 | 1.4% (0.3, 4.2) | 74/218 | 33.9% (27.7, 40.6)
Proximal DVT | 2/221 | 0.9% (0.1, 3.2) | 35/222 | 15.8% (11.2, 21.2)
Symptomatic VTE (all) | 1/326 | 0.3% [P value versus placebo = 0.021.] (0, 1.7) | 9/330 | 2.7% (1.3, 5.1)
Symptomatic PE | 0/326 | 0% [P value versus placebo = NS.] (0, 1.1) | 3/330 | 0.9% (0.2, 2.6)

14.3 Prophylaxis of Thromboembolic Events Following Hip Replacement Surgery in Adult Patients

In 2 randomized, double-blind, clinical trials in patients undergoing hip replacement surgery, ARIXTRA 2.5 mg subcutaneously once daily was compared to either enoxaparin sodium 30 mg subcutaneously every 12 hours (Study 1) or to enoxaparin sodium 40 mg subcutaneously once a day (Study 2). In Study 1, a total of 2,275 patients were randomized and 2,257 were treated. Patients ranged in age from 18 years to 92 years (mean age 65 years) with 48% men and 52% women. Patients were 94% Caucasian, 4% black, less than 1% Asian, and 2% others. In Study 2, a total of 2,309 patients were randomized and 2,273 were treated. Patients ranged in age from 24 years to 97 years (mean age 65 years) with 42% men and 58% women. Patients were 99% Caucasian, and 1% other races. Patients with serum creatinine level more than 2 mg/dL (180 micromol/L), or platelet count less than 100,000/mm^3 were excluded from both trials. In Study 1, ARIXTRA was initiated 6 ± 2 hours (mean 6.5 hours) after surgery in 92% of patients and enoxaparin sodium was initiated 12 hours to 24 hours (mean 20.25 hours) after surgery in 97% of patients. In Study 2, ARIXTRA was initiated 6 ± 2 hours (mean 6.25 hours) after surgery in 86% of patients and enoxaparin sodium was initiated 12 hours before surgery in 78% of patients. The first post-operative enoxaparin sodium dose was given within 12 hours after surgery in 60% of patients and 12 hours to 24 hours after surgery in 35% of patients with a mean of 13 hours. For both studies, both study treatments were continued for 7 ± 2 days. The efficacy data are provided in Table 12. Under the conditions of Study 1, ARIXTRA was associated with a VTE rate of 6.1% compared with a VTE rate of 8.3% for enoxaparin sodium for a relative risk reduction of 26% (95% CI: -11%, 53%; P = NS). Under the conditions of Study 2, fondaparinux sodium was associated with a VTE rate of 4.1% compared with a VTE rate of 9.2% for enoxaparin sodium for a relative risk reduction of 56% (95% CI: 33%, 73%; P <0.001). For the 2 studies combined, the major bleeding episodes occurred in 3% of patients receiving ARIXTRA and 2.1% of enoxaparin sodium patients [see Adverse Reactions (6.1)].

Table 12. Efficacy of ARIXTRA in the Prophylaxis of Thromboembolic Events Following Hip Replacement Surgery
Endpoint | Study 1; n/N [N = all evaluable hip replacement surgery patients. Evaluable patients were those who were treated and underwent the appropriate surgery (i.e., hip replacement surgery), with an adequate efficacy assessment up to Day 11.]; % (95% CI) |  | Study 2; n/N; % (95% CI)
Endpoint | ARIXTRA; 2.5 mg subcutaneously; once daily | Enoxaparin; Sodium; 30 mg subcutaneously; every 12 hr | ARIXTRA; 2.5 mg subcutaneously; once daily | Enoxaparin; Sodium; 40 mg subcutaneously; once daily
VTE [VTE was a composite of documented DVT and/or documented symptomatic PE reported up to Day 11.] | 48/787; 6.1% [P value versus enoxaparin sodium: NS.] (4.5, 8) | 66/797; 8.3% (6.5, 10.4) | 37/908; 4.1% [P value versus enoxaparin sodium in study 2: <0.001.] (2.9, 5.6) | 85/919; 9.2% (7.5, 11.3)
All DVT | 44/784; 5.6% [P value versus enoxaparin sodium in study 1: <0.05.] (4.1, 7.5) | 65/796; 8.2% (6.4, 10.3) | 36/908; 4.0% (2.8, 5.4) | 83/918; 9.0% (7.3, 11.1)
Proximal DVT | 14/816; 1.7% (0.9, 2.9) | 10/830; 1.2% (0.6, 2.2) | 6/922; 0.7% [P value versus enoxaparin sodium in study 2: <0.01.] (0.2, 1.4) | 23/927; 2.5% (1.6, 3.7)
Symptomatic PE | 5/1,126; 0.4% (0.1, 1) | 1/1,128; 0.1% (0, 0.5) | 2/1,129; 0.2% (0, 0.6) | 2/1,123; 0.2% (0, 0.6)

14.4 Prophylaxis of Thromboembolic Events Following Knee Replacement Surgery in Adult Patients

In a randomized, double-blind, clinical trial in patients undergoing knee replacement surgery (i.e., surgery requiring resection of the distal end of the femur or proximal end of the tibia), ARIXTRA 2.5 mg subcutaneously once daily was compared to enoxaparin sodium 30 mg subcutaneously every 12 hours. A total of 1,049 patients were randomized and 1,034 were treated. Patients ranged in age from 19 years to 94 years (mean age 68 years) with 41% men and 59% women. Patients were 88% Caucasian, 8% black, less 1% Asian, and 3% others. Patients with serum creatinine level more than 2 mg/dL (180 micromol/L), or platelet count less than 100,000/mm^3 were excluded from the trial. ARIXTRA was initiated 6 ± 2 hours (mean 6.25 hours) after surgery in 94% of patients, and enoxaparin sodium was initiated 12 hours to 24 hours (mean 21 hours) after surgery in 96% of patients. For both drugs, treatment was continued for 7 ± 2 days. The efficacy data are provided in Table 13 and demonstrate that under the conditions of the trial, ARIXTRA was associated with a VTE rate of 12.5% compared with a VTE rate of 27.8% for enoxaparin sodium for a relative risk reduction of 55% (95% CI: 36%, 70%; P <0.001). Major bleeding episodes occurred in 2.1% of patients receiving ARIXTRA and 0.2% of enoxaparin sodium patients [see Adverse Reactions (6.1)].

Table 13. Efficacy of ARIXTRA in the Prophylaxis of Thromboembolic Events Following Knee Replacement Surgery
Endpoint | ARIXTRA; 2.5 mg subcutaneously; once daily |  | Enoxaparin Sodium; 30 mg subcutaneously; every 12 hours
 | n/N [N = all evaluable knee replacement surgery patients. Evaluable patients were those who were treated and underwent the appropriate surgery (i.e., knee replacement surgery), with an adequate efficacy assessment up to Day 11.] | % (95% CI) | n/N | % (95% CI)
VTE [VTE was a composite of documented DVT and/or documented symptomatic PE reported up to Day 11.] | 45/361 | 12.5% [P value versus enoxaparin sodium <0.001.] (9.2, 16.3) | 101/363 | 27.8% (23.3, 32.7)
All DVT | 45/361 | 12.5% (9.2, 16.3) | 98/361 | 27.1% (22.6, 32)
Proximal DVT | 9/368 | 2.4% [P value versus enoxaparin sodium: NS.] (1.1, 4.6) | 20/372 | 5.4% (3.3, 8.2)
Symptomatic PE | 1/517 | 0.2% (0, 1.1) | 4/517 | 0.8% (0.2, 2)

14.5 Prophylaxis of Thromboembolic Events Following Abdominal Surgery in Patients at Risk for Thromboembolic Complications in Adult Patients

Abdominal surgery patients at risk included the following: Those undergoing surgery under general anesthesia lasting longer than 45 minutes who are older than 60 years with or without additional risk factors; and those undergoing surgery under general anesthesia lasting longer than 45 minutes who are older than 40 years with additional risk factors. Risk factors included neoplastic disease, obesity, chronic obstructive pulmonary disease, inflammatory bowel disease, history of deep vein thrombosis (DVT) or pulmonary embolism (PE), or congestive heart failure.

In a randomized, double-blind, clinical trial in patients undergoing abdominal surgery, ARIXTRA 2.5 mg subcutaneously once daily started postoperatively was compared to dalteparin sodium 5,000 IU subcutaneously once daily, with one 2,500 IU subcutaneously preoperative injection and a 2,500 IU subcutaneously first postoperative injection. A total of 2,927 patients were randomized and 2,858 were treated. Patients ranged in age from 17 years to 93 years (mean age 65 years) with 55% men and 45% women. Patients were 97% Caucasian, 1% black, 1% Asian, and 1% others. Patients with serum creatinine level more than 2 mg/dL (180 micromol/L), or platelet count less than 100,000/mm^3 were excluded from the trial. Sixty-nine percent (69%) of study patients underwent cancer-related abdominal surgery. Study treatment was continued for 7 ± 2 days. The efficacy data are provided in Table 14 and demonstrate that prophylaxis with ARIXTRA was associated with a VTE rate of 4.6% compared with a VTE rate of 6.1% for dalteparin sodium (P = NS).

Table 14. Efficacy of ARIXTRA in the Prophylaxis of Thromboembolic Events Following Abdominal Surgery
Endpoint | ARIXTRA; 2.5 mg subcutaneously; once daily |  | Dalteparin Sodium; 5,000 IU subcutaneously; once daily
 | n/N [N = all evaluable abdominal surgery patients. Evaluable patients were those who were randomized and had an adequate efficacy assessment up to Day 10; non-treated patients and patients who did not undergo surgery did not get a VTE assessment.] | % (95% CI) | n/N | % (95% CI)
VTE [VTE was a composite of venogram positive DVT, symptomatic DVT, non-fatal PE and/or fatal PE reported up to Day 10.] | 47/1,027 | 4.6% [P value versus dalteparin sodium: NS.] (3.4, 6) | 62/1,021 | 6.1% (4.7, 7.7)
All DVT | 43/1,024 | 4.2% (3.1, 5.6) | 59/1,018 | 5.8% (4.4, 7.4)
Proximal DVT | 5/1,076 | 0.5% (0.2, 1.1) | 5/1,077 | 0.5% (0.2, 1.1)
Symptomatic VTE | 6/1,465 | 0.4% (0.2, 0.9) | 5/1,462 | 0.3% (0.1, 0.8)

14.6 Treatment of Deep Vein Thrombosis in Adult Patients

In a randomized, double-blind, clinical trial in patients with a confirmed diagnosis of acute symptomatic DVT without PE, ARIXTRA 5 mg (body weight less than 50 kg), 7.5 mg (body weight 50 kg to 100 kg), or 10 mg (body weight greater than 100 kg) subcutaneously once daily (ARIXTRA treatment regimen) was compared to enoxaparin sodium 1 mg/kg subcutaneously every 12 hours. Almost all patients started study treatment in hospital. Approximately 30% of patients in both groups were discharged home from the hospital while receiving study treatment. A total of 2,205 patients were randomized and 2,192 were treated. Patients ranged in age from 18 years to 95 years (mean age 61 years) with 53% men and 47% women. Patients were 97% Caucasian, 2% black, and 1% other races. Patients with serum creatinine level more than 2 mg/dL (180 micromol/L), or platelet count less than 100,000/mm^3 were excluded from the trial. For both groups, treatment continued for at least 5 days with a treatment duration range of 7 ± 2 days, and both treatment groups received vitamin K antagonist therapy initiated within 72 hours after the first study drug administration and continued for 90 ± 7 days, with regular dose adjustments to achieve an INR of 2 to 3. The primary efficacy endpoint was confirmed, symptomatic, recurrent VTE reported up to Day 97. The efficacy data are provided in Table 15.

Table 15. Efficacy of ARIXTRA in the Treatment of Deep Vein Thrombosis (All Randomized)
Endpoint | ARIXTRA; 5 mg, 7.5 mg, or 10 mg; subcutaneously; once daily; N = 1,098 |  | Enoxaparin Sodium; 1 mg/kg; subcutaneously; every 12 hours; N = 1,107
 | n | % (95% CI) | n | % (95% CI)
Total VTE [VTE was a composite of symptomatic recurrent non-fatal VTE or fatal PE reported up to Day 97. The 95% confidence interval for the treatment difference for total VTE was: (-1.8% to 1.5%).] | 43 | 3.9% (2.8, 5.2) | 45 | 4.1% (3, 5.4)
DVT only | 18 | 1.6% (1, 2.6) | 28 | 2.5% (1.7, 3.6)
Non-fatal PE | 20 | 1.8% (1.1, 2.8) | 12 | 1.1% (0.6, 1.9)
Fatal PE | 5 | 0.5% (0.1, 1.1) | 5 | 0.5% (0.1, 1.1)

During the initial treatment period, 18 (1.6%) of patients treated with fondaparinux sodium and 10 (0.9%) of patients treated with enoxaparin sodium had a VTE endpoint (95% CI for the treatment difference [fondaparinux sodium-enoxaparin sodium] for VTE rates: -0.2%; 1.7%).

14.7 Treatment of Pulmonary Embolism in Adult Patients

In a randomized, open-label, clinical trial in patients with a confirmed diagnosis of acute symptomatic PE, with or without DVT, ARIXTRA 5 mg (body weight less than 50 kg), 7.5 mg (body weight 50 kg to 100 kg), or 10 mg (body weight greater than 100 kg) subcutaneously once daily (ARIXTRA treatment regimen) was compared to heparin IV bolus (5,000 USP units) followed by a continuous IV infusion adjusted to maintain 1.5 to 2.5 times aPTT control value. Patients with a PE requiring thrombolysis or surgical thrombectomy were excluded from the trial. All patients started study treatment in hospital. Approximately 15% of patients were discharged home from the hospital while receiving ARIXTRA therapy. A total of 2,213 patients were randomized and 2,184 were treated. Patients ranged in age from 18 years to 97 years (mean age 62 years) with 44% men and 56% women. Patients were 94% Caucasian, 5% black, and 1% other races. Patients with serum creatinine level more than 2 mg/dL (180 micromol/L), or platelet count less than 100,000/mm^3 were excluded from the trial. For both groups, treatment continued for at least 5 days with a treatment duration range 7 ± 2 days, and both treatment groups received vitamin K antagonist therapy initiated within 72 hours after the first study drug administration and continued for 90 ± 7 days, with regular dose adjustments to achieve an INR of 2 to 3. The primary efficacy endpoint was confirmed, symptomatic, recurrent VTE reported up to Day 97. The efficacy data are provided in Table 16.

Table 16. Efficacy of ARIXTRA in the Treatment of Pulmonary Embolism (All Randomized)
Endpoint | ARIXTRA; 5 mg, 7.5 mg, or 10 mg; subcutaneously; once daily; N = 1,103 |  | Heparin; aPTT adjusted IV; N = 1,110
 | n | % (95% CI) | n | % (95% CI)
Total VTE [VTE was a composite of symptomatic recurrent non-fatal VTE or fatal PE reported up to Day 97. The 95% confidence interval for the treatment difference for total VTE was: (-3% to 0.5%).] | 42 | 3.8% (2.8, 5.1) | 56 | 5% (3.8, 6.5)
DVT only | 12 | 1.1% (0.6, 1.9) | 17 | 1.5% (0.9, 2.4)
Non-fatal PE | 14 | 1.3% (0.7, 2.1) | 24 | 2.2% (1.4, 3.2)
Fatal PE | 16 | 1.5% (0.8, 2.3) | 15 | 1.4% (0.8, 2.2)

During the initial treatment period, 12 (1.1%) of patients treated with fondaparinux sodium and 19 (1.7%) of patients treated with heparin had a VTE endpoint (95% CI for the treatment difference [fondaparinux sodium-heparin] for VTE rates: -1.6%; 0.4%).

14.8 Treatment of Venous Thromboembolism in Pediatric Patients

The efficacy of ARIXTRA for the treatment of VTE in pediatric patients aged 1 year and older is based on an open-label, single-arm retrospective clinical study (FDPX-IJS-7001) in 366 pediatric patients aged 0.3 years to 17 years with VTE who were treated with fondaparinux sodium injection, including ARIXTRA, at a single center in a tertiary care pediatric hospital. Out of these 366 patients, 325 patients with diagnosis of VTE were included in the efficacy analysis set. Of the 325 total patients, 30 patients were less than 2 years, 65 patients were 2 years to less than 6 years, 78 patients were 6 years to less than 12 years, and 152 patients were 12 years to less than18 years. Patients were started on fondaparinux sodium injection 0.1 mg/kg once daily with doses rounded to the nearest prefilled syringe (2.5 mg, 5 mg, or 7.5 mg) for patients weighing over 20 kg. For patients weighing 10 kg to 20 kg, dosing was based on body weight without rounding to the nearest prefilled syringe. Fondaparinux levels were monitored after the second or third dose until therapeutic levels were achieved. Fondaparinux levels were then monitored weekly while patients were admitted within the hospital and, after approximately every 1 month to 3 months while outpatient for the duration of treatment. Dosing adjustments were made to achieve peak fondaparinux blood concentration within the therapeutic target of 0.5 mg/L to 1 mg/L.

Patients received an initial median dose of approximately 0.1 mg/kg body weight of fondaparinux sodium injection, which translates into a median dose of 1.37 mg in the less than 20 kg weight group, 2.5 mg in the 20 kg to less than 40 kg weight group, 5 mg in the 40 kg to less than 60 kg, and 7.5 mg in the greater than or equal to 60 kg weight group. Based on median values, it took approximately 3 days (range 1 day to 929 days) to achieve therapeutic levels across all age groups.

The efficacy of ARIXTRA was based on measuring the proportion of pediatric patients with complete clot resolution up to 3 months (±15 days). Among the 325 pediatric patients in the efficacy analysis set, 146 (44.9%; 95% CI: 39.6, 50.4) experienced complete resolution of at least one clot, while 143 (44%; 95% CI: 38.7, 49.4) had complete resolution of all clots. Summaries of complete clot resolution of patients’ main VTEs at month 3 are provided by age group (see Table 17) and weight group (see Table 18).

Table 17. Summary of Complete Clot Resolution of Main VTEs Up to Month 3 by Age Group
Parameter | Less than 2 years; (N=30); n (%) | Greater than or equal to 2 years to less than 6 years; (N=65); n (%) | Greater than or equal to 6 years to less than 12 years; (N=78); n (%) | Greater than or equal to 12 years to less than 18 years; (N=152); n (%)
Complete Resolution of At Least One Clot, n (%); 95% Confidence Interval | 14 (46.7); (30.2, 63.9) | 26 (40); (29, 52.1) | 40 (51.3); (40.4, 62.1) | 66 (43.4); (35.8, 51.4)
Complete Resolution of All Clots, n (%); 95% Confidence Interval | 14 (46.7); (30.2, 63.9) | 25 (38.5); (27.6, 50.6) | 39 (50); (39.2, 60.8) | 65 (42.8); (35.2, 50.7)

Table 18. Summary of Complete Clot Resolution of Main VTEs Up to Month 3 by Weight Group
Parameter | Less than 20 kg; (N=95); n (%) | 20 kg to less than 40 kg; (N=84); n (%) | 40 kg to less than 60 kg; (N=72); n (%) | Greater than or equal to 60 kg; (N=73); n (%)
Complete Resolution of At Least One Clot, n (%); 95% Confidence Interval | 42 (44.2); (34.6, 54.2) | 45 (53.6); (43, 63.8) | 30 (41.7); (31, 53.2) | 28 (38.4); (28.1, 49.8)
Complete Resolution of All Clots, n (%); 95% Confidence Interval | 41 (43.2); (33.7, 53.2) | 45 (53.6); (43, 63.8) | 29 (40.3); (29.7, 51.8) | 27 (37); (26.8, 48.5)

16 HOW SUPPLIED/STORAGE AND HANDLING

ARIXTRA (fondaparinux sodium injection, USP) is available in single-dose, prefilled syringes containing clear to practically clear and colorless liquid in the following strengths:

2.5 mg/0.5 mL ARIXTRA in single-dose prefilled syringe, affixed with a 27-gauge x ½-inch needle and an automatic needle protection system with white plunger rod.

NDC 67457-592-10 10 Single Unit Syringes

5 mg/0.4 mL ARIXTRA in single-dose prefilled syringe, affixed with a 27-gauge x ½-inch needle and an automatic needle protection system with white plunger rod.

NDC 67457-593-04 10 Single Unit Syringes

7.5 mg/0.6 mL ARIXTRA in single-dose prefilled syringe, affixed with a 27-gauge x ½-inch needle and an automatic needle protection system with white plunger rod.

NDC 67457-594-06 10 Single Unit Syringes

10 mg/0.8 mL ARIXTRA in single-dose prefilled syringe, affixed with a 27-gauge x ½-inch needle and an automatic needle protection system with white plunger rod.

NDC 67457-595-08 10 Single Unit Syringes

Store at 20°C to 25°C (68°F to 77°F); excursions permitted between 15°C to 30°C (59°F to 86°F) [See USP Controlled Room Temperature].

Discard unused portion.

PHARMACIST: Dispense a Patient Information Leaflet with each prescription.

17 PATIENT COUNSELING INFORMATION

Advise the patient to read the FDA-approved patient labeling (Patient Information and Instructions for Use).

17.1 Patient Advice

If the patients have had neuraxial anesthesia or spinal puncture, and particularly, if they are taking concomitant NSAIDS, platelet inhibitors, or other anticoagulants, inform patients to watch for signs and symptoms of spinal or epidural hematomas, such as back pain, tingling, numbness (especially in the lower limbs), muscular weakness, and stool or urine incontinence. If any of these symptoms occur, advise patients to contact his or her physician immediately.

The use of aspirin and other NSAIDS may enhance the risk of hemorrhage. Advise patients to discontinue use prior to ARIXTRA therapy whenever possible; if co-administration is essential, the patient’s clinical and laboratory status should be closely monitored [see Drug Interactions (7)].

If patients must self-administer ARIXTRA or if administered by a caregiver, (e.g., if ARIXTRA is used at home), advise patients of the following:

- Advise patients that ARIXTRA should be given by subcutaneous injection. Instruct patients in the proper technique for administration.
- Instruct patients that if they miss a dose of ARIXTRA, to inject the dose as soon as they remember. Advise patients not to inject two doses at the same time.
- The most important risk with ARIXTRA administration is bleeding. Counsel patients on signs and symptoms of possible bleeding.
- Advise patients that it may take them longer than usual to stop bleeding.
- Advise patients that they may bruise and/or bleed more easily when they are treated with ARIXTRA.
- Advise patients to report any unusual bleeding, bruising, or signs of thrombocytopenia (such as a rash of dark red spots under the skin) to their physician [see Warnings and Precautions (5.2, 5.5)].
- Advise patients to tell their physicians and dentists they are taking ARIXTRA and/or any other product known to affect bleeding before any surgery is scheduled and before any new drug is taken [see Warnings and Precautions (5.2)].
- Advise patients to tell their physicians and dentists of all medications they are taking, including those obtained without a prescription, such as aspirin or other NSAIDs [see Drug Interactions (7)].

Manufactured for:
Mylan Institutional LLC
Morgantown, WV 26505 U.S.A.

Manufactured by:
Aspen Notre Dame de Bondeville
Notre Dame de Bondeville, France

MI:ARXTIJ:R7p

PATIENT INFORMATION

ARIXTRA® (Ah-RIX-trah)

(fondaparinux sodium injection)

for subcutaneous use

What is the most important information I should know about ARIXTRA?

ARIXTRA may cause serious side effects, including:

- Spinal or epidural blood clots (hematoma). People who take a blood thinner medicine (anticoagulant) like ARIXTRA, and have medicine injected into their spinal and epidural area, or have a spinal puncture have a risk of forming a blood clot that can cause long-term or permanent loss of the ability to move (paralysis). Your risk of developing a spinal or epidural blood clot is higher if:
  - a thin tube called an epidural catheter is placed in your back to give you certain medicine
  - you take non-steroidal anti-inflammatory drugs (NSAIDs) or a medicine to help prevent blood from clotting
  - you have a history of difficult or repeated epidural or spinal punctures
  - you have a history of problems with your spine or have had surgery on your spine
If you use ARIXTRA and receive spinal anesthesia or have a spinal puncture, your doctor should watch you closely for symptoms of spinal or epidural blood clots. Tell your doctor right away if you have back pain, tingling, numbness, muscle weakness (especially in your legs and feet), and loss of control of your bowels or bladder (incontinence).
Because the risk of bleeding may be higher, tell your doctor before using ARIXTRA if you:
  1. are also taking certain other medicines that affect blood clotting such as aspirin, an NSAID (for example, ibuprofen or naproxen), clopidogrel, or warfarin sodium
  2. have bleeding problems
  3. had problems in the past with pain medication given through the spine
  4. have had surgery to your spine
  5. have a spinal deformity

See “What are the possible side effects of ARIXTRA?” for more information about side effects.

What is ARIXTRA?

ARIXTRA is a prescription medicine that is used to:

- help prevent blood clots from forming in adults who have had certain surgeries of the hip, knee, or the stomach-area (abdominal surgery).
- treat adults who have blood clots in their legs or blood clots that travel to their lungs, along with the blood thinner medicine called warfarin sodium.
- treat children 1 year of age or older weighing at least 22 pounds (10 kg) who have blood clots.

It is not known if ARIXTRA is safe and effective for use in children:

- younger than 1 year of age and weighing less than 22 pounds (10 kg) who have blood clots.
- younger than 1 year of age with kidney problems.
- for the prevention of blood clots in the legs and to treat blood clots in the legs or lungs when given with warfarin sodium.
- with liver problems.

Who should not use ARIXTRA?

Do not use ARIXTRA if you:

- have certain kidney problems
- have active bleeding problems
- have an infection in your heart
- have low platelet counts and if you test positive for a certain antibody during treatment with ARIXTRA
- weigh less than 110 pounds (50 kg) and ARIXTRA will be used to help prevent blood clots in adults undergoing certain surgery. See “What are the possible side effects of ARIXTRA?”
- had a serious allergic reaction to ARIXTRA

Before using ARIXTRA, tell your doctor about all of your medical conditions, including if you:

- have had any bleeding problems (such as stomach ulcers)
- have had a stroke
- have had recent surgeries, including eye surgery
- have diabetic eye disease
- have kidney or liver problems
- have uncontrolled high blood pressure
- have a latex allergy. The packaging (needle guard) for ARIXTRA contains dry natural latex rubber.
- are pregnant or plan to become pregnant. ARIXTRA may harm your unborn baby. If you are pregnant, talk to your doctor about the best way for you to prevent or treat blood clots.
- are breastfeeding or plan to breastfeed. It is not known if ARIXTRA passes into breast milk. You and your doctor should decide if you will breastfeed during treatment with ARIXTRA.

Tell your doctor about all the medicines you take including prescriptions and over-the-counter medicines, vitamins, and herbal supplements. Some medicines can increase your risk of bleeding.

See “What is the most important information I should know about ARIXTRA?” Do not start taking any new medicines without first talking to your doctor.

Tell all your doctors and dentist that you use ARIXTRA, especially if you need to have any kind of surgery or a dental procedure. Keep a list of your medicines and show it to all your doctors and pharmacist before you start a new medicine.

How should I use ARIXTRA?

- ARIXTRA is available in different types of syringes. Your doctor will decide which type of syringe is best for you or your child. See the Instructions for Use to confirm the prescribed syringe and how to give an ARIXTRA injection.
- If your doctor tells you that you may give yourself or your child injections of ARIXTRA at home, you will be shown how to give the injections first before you do them on your own.
- Use ARIXTRA exactly as your doctor tells you to.
- ARIXTRA is given as an injection under your skin (subcutaneous injection).
- If you miss a dose of ARIXTRA, inject your dose as soon as you remember. Do not inject 2 doses at the same time.
- Your doctor may perform blood tests and test for blood in your stool as needed during treatment with ARIXTRA to check for side effects.
- If you inject too much ARIXTRA, call your doctor right away.

What are possible side effects of ARIXTRA?

ARIXTRA can cause serious side effects. See “What is the most important information I should know about ARIXTRA?”

- Severe bleeding. Certain conditions can increase your risk for severe bleeding, including:
  - some bleeding problems
  - some gastrointestinal problems including ulcers
  - some types of strokes
  - uncontrolled high blood pressure
  - diabetic eye disease
  - soon after brain, spine, or eye surgery
In children, certain conditions that can increase risk of bleeding, include:
  1. systemic lupus erythematous (also known as Lupus)
  2. Wilms tumor
  3. antiphospholipid syndrome
  4. genetic conditions that affect blood clotting
  5. cancer
  6. decreased red blood cells, white blood cells and platelets (pancytopenia)
  7. indwelling chest tubes
  8. chest surgery
  9. infection
  10. severe high blood pressure that affects the brain
  11. enlarged or blocked lymph vessels in the small intestine (intestinal lymphangiectasia)
- Certain kidney problems can also increase your risk of bleeding with ARIXTRA. Your doctor may check your kidney function during your treatment with ARIXTRA.
- Increased bleeding risk in adults who weigh less than 110 pounds (50 kg) undergoing certain surgeries.
- Low blood platelets (thrombocytopenia). Platelets are blood cells that help your blood to clot normally. Your doctor may check your platelet counts during your treatment with ARIXTRA.
  You may bruise or bleed more easily during your treatment with ARIXTRA, and it may take longer than usual for bleeding to stop. Tell your doctor if you have any signs or symptoms of bleeding, bruising or rash of dark red spots under the skin during your treatment with ARIXTRA.

The most common side effects of ARIXTRA in adults include:

- bleeding problems
- bleeding, rash, and itching at the injection site (injection site reactions)
- increased blood levels of certain liver tests
- low red blood cell counts (anemia)
- sleep problems (insomnia)
- increased wound drainage
- low potassium in your blood (hypokalemia)
- dizziness

- purplish spots on skin (purpura)
- low blood pressure (hypotension)
- confusion
- fluid-filled blisters (bullous eruption)
- blood clots (hematoma)
- severe bleeding after surgery (post-operative hemorrhage)
- infection

The most common side effects of ARIXTRA in children include:

- bleeding problems
- low red blood cell counts (anemia)
- low blood platelet counts
- allergic reaction, such as sudden swelling of your face, tongue, throat, or trouble swallowing

- skin problems
- abnormal blood levels of certain liver tests
- low potassium in your blood (hypokalemia)
- low blood pressure (hypotension)

These are not all the possible side effects of ARIXTRA.

Call your doctor for medical advice about side effects. You may report side effects to FDA at 1-800-FDA-1088.

How should I store ARIXTRA?

- See the product label for complete instructions on how to store ARIXTRA.
- Throw away (discard) ARIXTRA that is out of date (expired) or unused.

Keep ARIXTRA and all medicines out of the reach of children.

General information about the safe and effective use of ARIXTRA

Medicines are sometimes prescribed for purposes other than those listed in Patient Information leaflets. Do not use ARIXTRA for a condition for which it was not prescribed. Do not give ARIXTRA to other people, even if they have the same symptoms that you have. It may harm them.

You can ask your pharmacist or doctor for information about ARIXTRA that is written for healthcare professionals.

What are the ingredients in ARIXTRA?

Active ingredient: fondaparinux sodium

Inactive ingredients: sodium chloride and water for injection. May also contain sodium hydroxide and/or hydrochloric acid as pH adjusters.

Manufactured for:
Mylan Institutional LLC
Morgantown, WV 26505 U.S.A.

Manufactured by:
Aspen Notre Dame de Bondeville
Notre Dame de Bondeville, France

For more information about ARIXTRA, contact Mylan at 1-877-446-3679 (1-877-4-INFO-RX).

This Patient Information has been approved by the U.S. Food and Drug Administration.

Revised: 12/2024

MI:PL:ARXTIJ:R7p

INSTRUCTIONS FOR USE

ARIXTRA® (Ah-RIX-trah)
(fondaparinux sodium injection)
for subcutaneous use

This Instructions for Use contains information on how to inject ARIXTRA. Before you use ARIXTRA, read and follow the step-by-step instructions. Talk to your or your child’s doctor or pharmacist if you have any questions.

Important Information You Need to Know Before Injecting ARIXTRA

- ARIXTRA is available in different types of syringes. Confirm the syringe looks like the figure below before you continue:

- Your healthcare provider should show you how to prepare and inject ARIXTRA. Do not inject yourself or someone else until you have been shown how to inject ARIXTRA.
- Each ARIXTRA syringe is 1 dose of ARIXTRA. The syringe is for a one-time use only.
- Use ARIXTRA exactly as prescribed by your doctor.
- The packaging (needle guard) for ARIXTRA contains dry natural latex rubber.

How should I store ARIXTRA syringes?

- Store ARIXTRA at room temperature between 68°F to 77°F (20°C to 25°C).
- Keep ARIXTRA syringes and all medicines out of the reach of children.

Do not use ARIXTRA if:

- the solution appears discolored (the solution should normally appear clear)
- you see any particles in the solution
- the syringe is damaged
- it is out of date (expired)

How should I give an injection of ARIXTRA?

ARIXTRA is injected into a skinfold of the lower stomach-area (abdomen) as directed by your or your child’s doctor. Do not inject ARIXTRA into muscle.

Instructions for injecting ARIXTRA

Parts of the ARIXTRA syringe:

1. Rigid needle guard
2. Plunger
3. Finger-grip
4. Security sleeve

Syringe Before Use

Syringe After Use

1. Wash your hands well with soap and water, rinse, and towel dry.

2. Sit or lie down in a comfortable position. If giving the injection to a child, instruct child to sit or lie down in a comfortable position. Choose a spot on the lower stomach-area (abdomen), at least 2 inches below the belly button (Figure A). Change (alternate) between using the left and right side of the lower abdomen for each injection.

Figure A.

3. Clean the injection area with an alcohol swab.

4. Remove the needle guard, by first twisting it counter-clockwise and then pulling it in a straight line away from the body of the syringe (Figure B). Throw away (discard) the needle guard.
  1. Do not touch the needle or let it come in contact with any surface before the injection. A small air bubble in the syringe is normal.
  2. To be sure that you do not lose any medicine from the syringe, do not try to remove air bubbles from the syringe before giving the injection.

Figure B.

5. Gently pinch the skin that has been cleaned to make a fold. Hold the fold between the thumb and the forefinger of one hand during the entire injection (Figure C).

Figure C.

6. Hold the syringe firmly in your other hand using the finger grip. Insert the full length of the needle straight into your skinfold at an angle of 90° (Figure D).

Figure D.

7. Inject all of the medicine in the syringe by using your thumb to firmly press down on the plunger as far as it goes. This will activate the automatic needle protection system (Figure E).

Figure E.

8. Release the plunger.
  1. The needle will withdraw automatically from the skin and pull back (retract) into the security sleeve where it will be locked (Figure F).
  2. A white safety indicator will appear above the upper body of the syringe.
  3. You may hear or feel a soft click after the plunger rod is released.

Figure F.

9. Throw away (dispose of) used and unused ARIXTRA syringes:
2. Put your used ARIXTRA needles and syringes in an FDA-cleared sharps disposal container right away after use. Do not throw away (dispose of) loose needles and syringes in your household trash.
3. If you do not have an FDA-cleared sharps disposal container, you may use a household container that is:
  - made of a heavy-duty plastic,
  - can be closed with a tight-fitting, puncture-resistant lid, without sharps being able to come out,
  - upright and stable during use,
  - leak-resistant, and
  - properly labeled to warn of hazardous waste inside the container.
4. When your sharps disposal container is almost full, you will need to follow your community guidelines for the right way to dispose of your sharps disposal container. There may be state or local laws about how you should throw away used needles and syringes. For more information about safe sharps disposal, and for specific information about sharps disposal in the state that you live in, go to the FDA's website at: http://www.fda.gov/safesharpsdisposal.
5. Do not dispose of your used sharps disposal container in your household trash unless your community guidelines permit this. Do not recycle your used sharps disposal container.

This Instructions for Use has been approved by the U.S. Food and Drug Administration Revised: 12/2024

Manufactured for:
Mylan Institutional LLC
Morgantown, WV 26505 U.S.A.

Manufactured by:
Aspen Notre Dame de Bondeville
Notre Dame de Bondeville, France

MI:IFU1:ARXTIJ:R7p

INSTRUCTIONS FOR USE

ARIXTRA® (Ah-RIX-trah)
(fondaparinux sodium injection)
for subcutaneous use

This Instructions for Use contains information on how to inject ARIXTRA. Before you use ARIXTRA, read and follow the step-by-step instructions. Talk to your child’s doctor or pharmacist if you have any questions.

Important Information You Need to Know Before Injecting ARIXTRA

- ARIXTRA is available in different types of syringes. Confirm the syringe looks like the figure below before you continue:

- Your healthcare provider should show you how to prepare and inject ARIXTRA. Do not inject your child until you have been shown how to inject ARIXTRA.
- Each ARIXTRA syringe is 1 dose of ARIXTRA. The syringe is for a one-time use only.
- Use ARIXTRA exactly as prescribed by your doctor.

How should I store ARIXTRA syringes?

- Store ARIXTRA syringes in a refrigerator between 36°F to 46°F (2°C to 8°C) for up to the beyond use date on the syringe.
- Do not freeze.
- Store syringes in a clean container in the refrigerator.
- Do not store ARIXTRA syringes at room temperature between 68°F to 77°F (20°C to 25°C).
- Take ARIXTRA syringe out of the refrigerator and allow it to reach room temperature. Inject right away after the syringe reaches room temperature.
- Throw away (dispose of) ARIXTRA syringes that has been left at room temperature for longer than 4 hours.
- Keep ARIXTRA syringes and all medicines out of the reach of children.

Do not use ARIXTRA if:

- the solution appears discolored (the solution should normally appear clear)
- you see any particles in the solution
- the syringe is damaged, including:
  - cracks, breaks, or bends in the syringe or the plunger
  - broken, bent, or detached needle
  - medicine leaking from the plunger or needle
- past the beyond use date on the syringe labeled by the pharmacy

How should I give an injection of ARIXTRA?

ARIXTRA is injected into a skin fold of the lower stomach-area (abdomen) as directed by your child’s doctor. Do not inject ARIXTRA into muscle.

Instructions for injecting ARIXTRA

Parts of the ARIXTRA syringe:

1. Rigid needle guard
2. Finger-grip
3. Plunger

1. Wash your hands well with soap and water, rinse, and towel dry.

2. Instruct your child to sit or lie down in a comfortable position. Choose a spot on the lower stomach-area (abdomen), at least 2 inches below the belly button (Figure A). Change (alternate) between using the left and right side of the lower abdomen for each injection

Figure A.

3. Clean the injection area with an alcohol swab.

4. Remove the needle guard, by pulling it in a straight line away from the body of the syringe (Figure B). Throw away (discard) the needle guard.
  1. Do not touch the needle or let it come in contact with any surface before the injection. A small air bubble in the syringe is normal.
  2. To be sure that you do not lose any medicine from the syringe, do not try to remove air bubbles from the syringe before giving the injection.

Figure B.

5. Gently pinch the skin that has been cleaned to make a fold. Hold the fold between the thumb and the forefinger of one hand during the entire injection (Figure C).

Figure C.

6. Hold the syringe firmly in your other hand using the finger grip. Insert the full length of the needle straight down into your skinfold (at an angle of 90°) (Figure D).

Figure D.

7. Inject all of the medicine in the syringe by using your thumb to firmly press down on the plunger as far as it goes (Figure E).

Figure E.

8. Pull out the needle at the same angle you inserted in (Figure F).

Figure F.

9. Throw away (dispose of) used and unused ARIXTRA needles and syringes:
2. Put your used ARIXTRA needles and syringes in an FDA-cleared sharps disposal container right away after use. Do not throw away (dispose of) loose needles and syringes in your household trash.
3. If you do not have an FDA-cleared sharps disposal container, you may use a household container that is:
  - made of a heavy-duty plastic,
  - can be closed with a tight-fitting, puncture-resistant lid, without sharps being able to come out,
  - upright and stable during use,
  - leak-resistant, and
  - properly labeled to warn of hazardous waste inside the container.
4. When your sharps disposal container is almost full, you will need to follow your community guidelines for the right way to dispose of your sharps disposal container. There may be state or local laws about how you should throw away used needles and syringes. For more information about safe sharps disposal, and for specific information about sharps disposal in the state that you live in, go to the FDA's website at: http://www.fda.gov/safesharpsdisposal.
5. Do not dispose of your used sharps disposal container in your household trash unless your community guidelines permit this. Do not recycle your used sharps disposal container.

This Instructions for Use has been approved by the U.S. Food and Drug Administration Revised: 12/2024

Manufactured for:
Mylan Institutional LLC
Morgantown, WV 26505 U.S.A.

Manufactured by:
Aspen Notre Dame de Bondeville
Notre Dame de Bondeville, France

MI:IFU2:ARXTIJ:R1p

PRINCIPAL DISPLAY PANEL – 2.5 mg/0.5 mL

NDC 67457-592-10

Arixtra®
(fondaparinux sodium injection, USP)

2.5 mg/0.5 mL

For Subcutaneous Injection
PHARMACIST: Dispense the accompanying Patient Information

Leaflet to each patient.

Rx only

Contains 10 Single-Dose, Prefilled Syringes
Affixed with an Automatic Needle Protection System

Contents: Each single-dose prefilled syringe contains 2.5 mg of fondaparinux sodium, USP in 0.5 mL of an isotonic solution of sodium chloride and water for injection. May also contain sodium hydroxide and/or hydrochloric acid as pH adjusters.

The needle guard of the prefilled syringe of ARIXTRA contains dry natural latex rubber that may cause allergic reactions in latex sensitive individuals.

Recommended Dose: 2.5 mg subcutaneous injection, once daily. See package insert.

Storage: Store at 20°C to 25°C (68°F to 77°F); excursions permitted between 15°C to 30°C (59°F to 86°F) [See USP Controlled Room Temperature].

Discard unused portion.

Manufactured for:
Mylan Institutional LLC
Morgantown, WV 26505 U.S.A.

Made in France

MI:592:10C:R6

Mylan.com

PRINCIPAL DISPLAY PANEL – 5 mg/0.4 mL

NDC 67457-593-04

Arixtra®

(fondaparinux sodium injection, USP)

5 mg/0.4 mL

For Subcutaneous Injection

PHARMACIST: Dispense the accompanying Patient Information
Leaflet to each patient.

Rx only

Contains 10 Single-Dose, Prefilled Syringes
Affixed with an Automatic Needle Protection System

Contents: Each single-dose prefilled syringe contains 5 mg of fondaparinux sodium, USP
in 0.4 mL of an isotonic solution of sodium chloride and water for injection. May also
contain sodium hydroxide and/or hydrochloric acid as pH adjusters.

The needle guard of the prefilled syringe of ARIXTRA contains dry natural latex rubber that
may cause allergic reactions in latex sensitive individuals.

Recommended Dose: 5 mg subcutaneous injection, once daily. See package insert.

Storage: Store at 20°C to 25°C (68°F to 77°F); excursions permitted between 15°C to 30°C (59°F to 86°F) [See USP Controlled Room Temperature].

Discard unused portion.

Manufactured for:
Mylan Institutional LLC
Morgantown, WV 26505 U.S.A.

Made in France

MI:593:10C:R6

Mylan.com

PRINCIPAL DISPLAY PANEL – 7.5 mg/0.6 mL

NDC 67457-594-06

Arixtra®

(fondaparinux sodium injection, USP)

7.5 mg/0.6 mL

For Subcutaneous Injection

PHARMACIST: Dispense the accompanying Patient Information
Leaflet to each patient.

Rx only

Contains 10 Single-Dose, Prefilled Syringes

Affixed with an Automatic Needle Protection System

Contents: Each single-dose prefilled syringe contains 7.5 mg of fondaparinux sodium, USP
in 0.6 mL of an isotonic solution of sodium chloride and water for injection. May also
contain sodium hydroxide and/or hydrochloric acid as pH adjusters.

The needle guard of the prefilled syringe of ARIXTRA contains dry natural latex rubber that
may cause allergic reactions in latex sensitive individuals.

Recommended Dose: 7.5 mg subcutaneous injection, once daily. See package insert.

Storage: Store at 20°C to 25°C (68°F to 77°F); excursions permitted between 15°C to 30°C (59°F to 86°F) [See USP Controlled Room Temperature].

Discard unused portion.

Manufactured for:
Mylan Institutional LLC
Morgantown, WV 26505 U.S.A.

Made in France

MI:594:10C:R6

Mylan.com

PRINCIPAL DISPLAY PANEL – 10 mg/0.8 mL

NDC 67457-595-08

Arixtra®

(fondaparinux sodium injection, USP)

10 mg/0.8 mL

For Subcutaneous Injection

PHARMACIST: Dispense the accompanying Patient Information
Leaflet to each patient.

Rx only

Contains 10 Single-Dose, Prefilled Syringes
Affixed with an Automatic Needle Protection System

Contents: Each single-dose prefilled syringe contains 10 mg of fondaparinux sodium, USP
in 0.8 mL of an isotonic solution of sodium chloride and water for injection. May also
contain sodium hydroxide and/or hydrochloric acid as pH adjusters.

The needle guard of the prefilled syringe of ARIXTRA contains dry natural latex rubber that
may cause allergic reactions in latex sensitive individuals.

Recommended Dose: 10 mg subcutaneous injection, once daily. See package insert.

Storage: Store at 20°C to 25°C (68°F to 77°F); excursions permitted between 15°C to 30°C (59°F to 86°F) [See USP Controlled Room Temperature].

Discard unused portion.

Manufactured for:
Mylan Institutional LLC
Morgantown, WV 26505 U.S.A.

Made in France

MI:595:10C:R6

Mylan.com